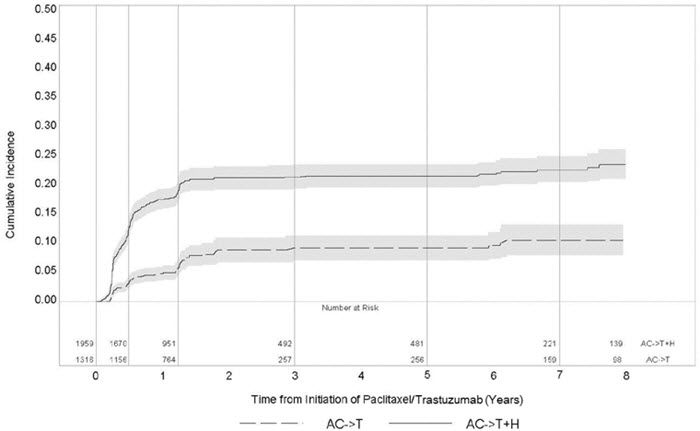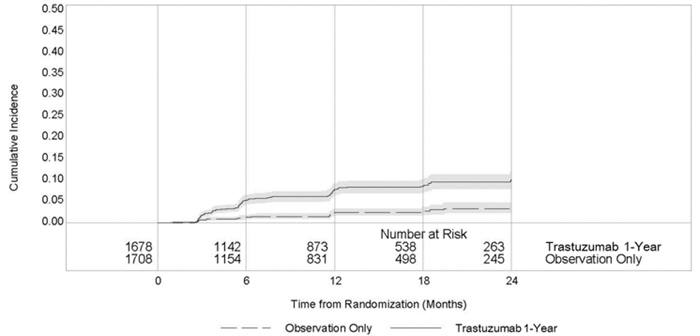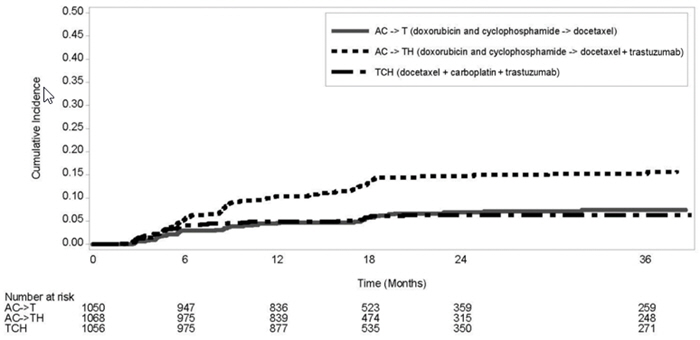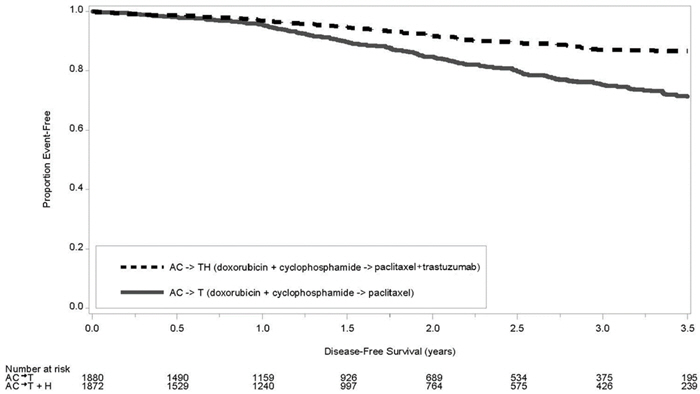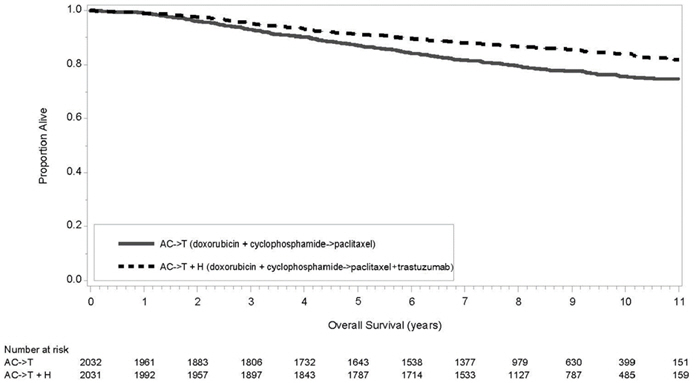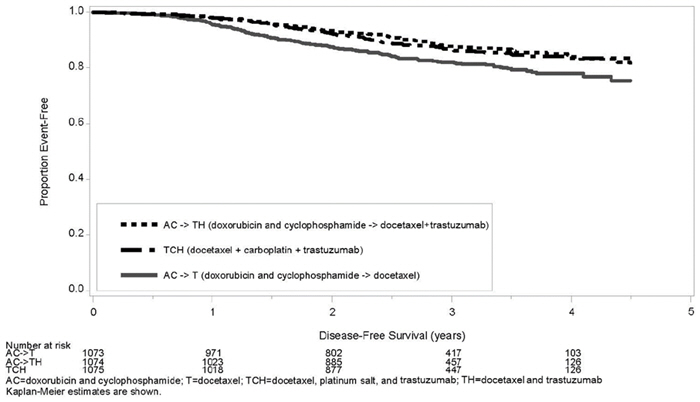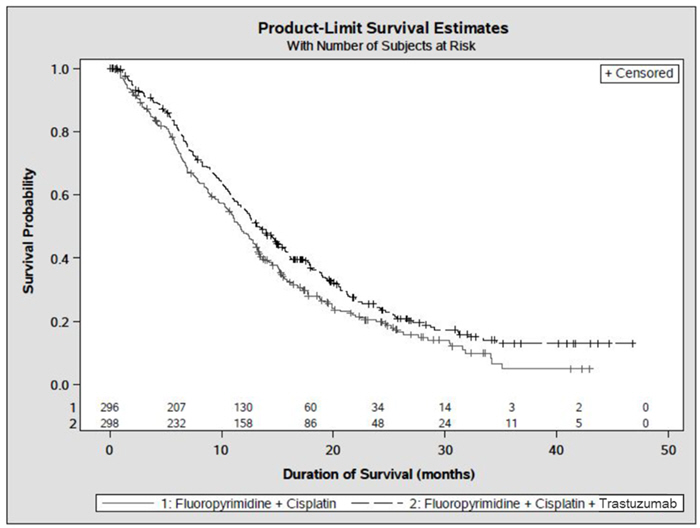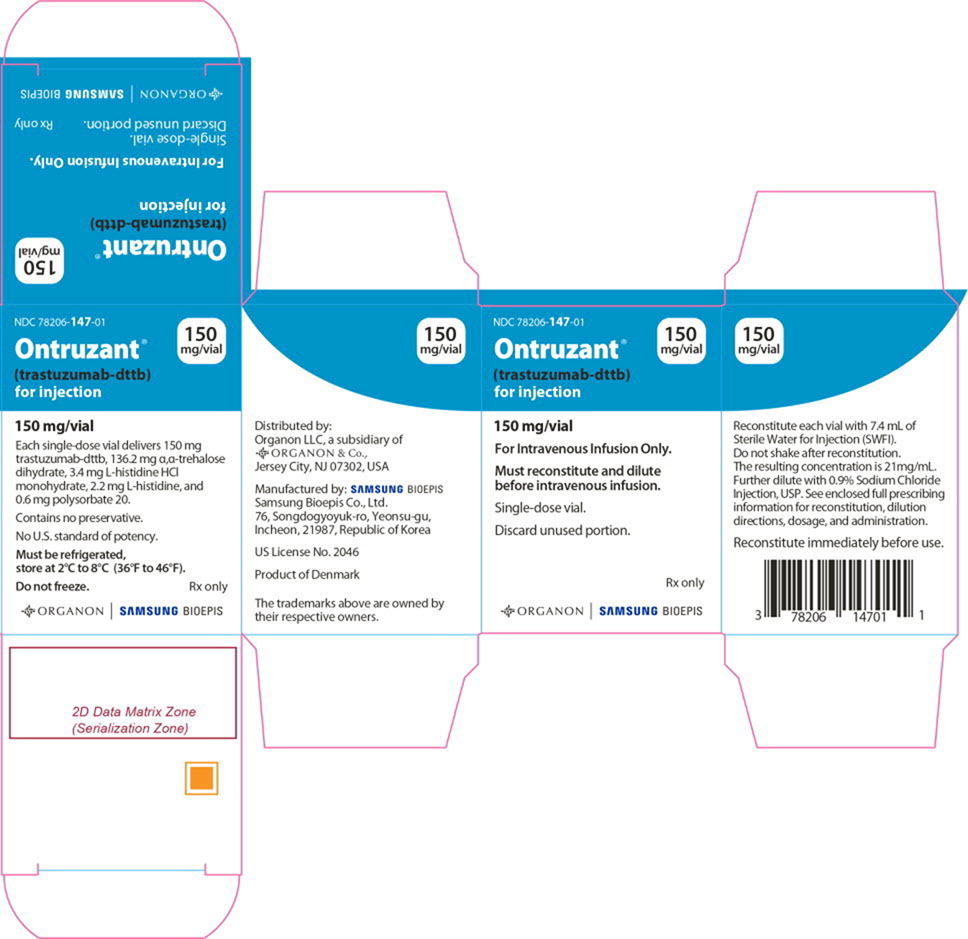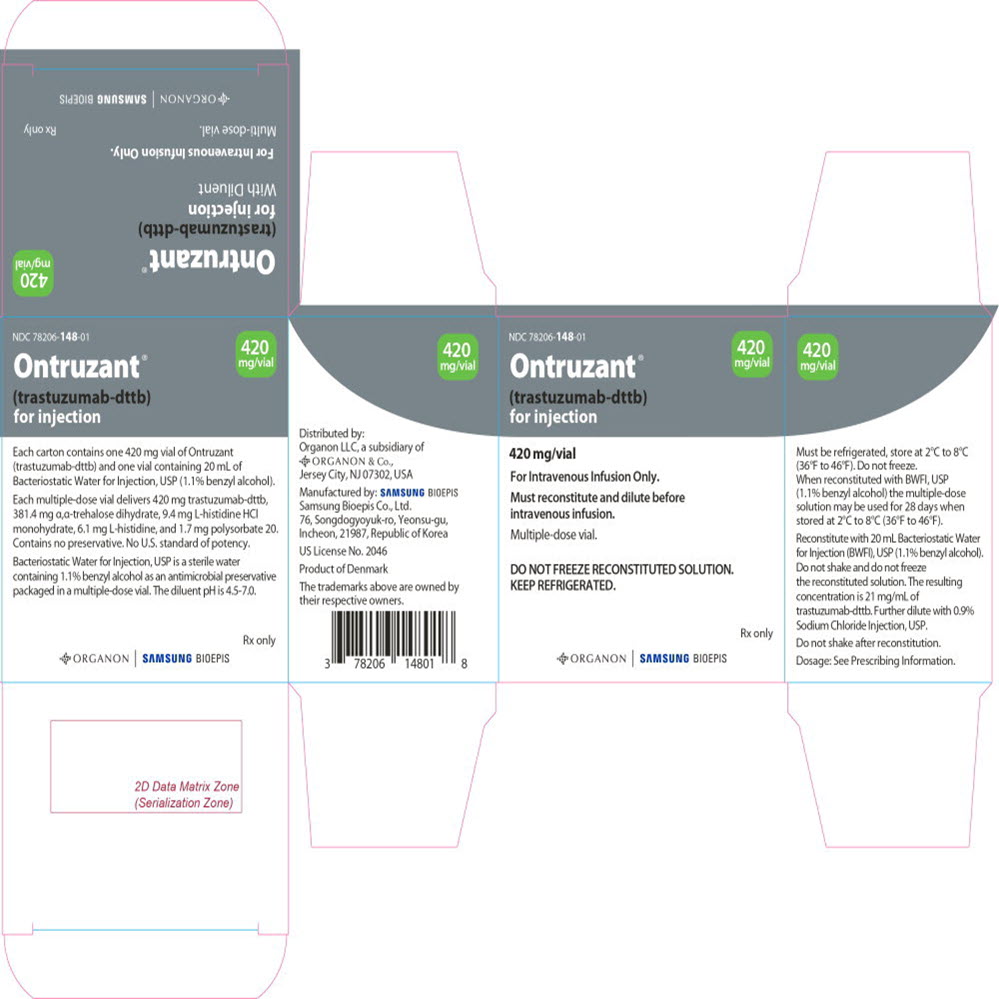 DRUG LABEL: Ontruzant
NDC: 78206-147 | Form: INJECTION, POWDER, LYOPHILIZED, FOR SOLUTION
Manufacturer: Organon LLC
Category: prescription | Type: HUMAN PRESCRIPTION DRUG LABEL
Date: 20250311

ACTIVE INGREDIENTS: trastuzumab 150 mg/1 1
INACTIVE INGREDIENTS: trehalose dihydrate 136.2 mg/1 1; histidine monohydrochloride monohydrate; histidine; polysorbate 20

HIGHLIGHTS OF PRESCRIBING INFORMATION

These highlights do not include all the information needed to use ONTRUZANT safely and effectively. See full prescribing information for ONTRUZANT.
ONTRUZANT (trastuzumab-dttb) for injection, for intravenous use
Initial U.S. Approval: 2019
ONTRUZANT (trastuzumab-dttb) is biosimilar [Biosimilar means that the biological product is approved based on data demonstrating that it is highly similar to an FDA-approved biological product, known as a reference product, and that there are no clinically meaningful differences between the biosimilar product and the reference product. Biosimilarity of Ontruzant has been demonstrated for the condition(s) of use (e.g. indication(s), dosing regimen(s)), strength(s), dosage form(s), and route(s) of administration described in its Full Prescribing Information.] to HERCEPTIN (trastuzumab)

WARNING: CARDIOMYOPATHY, INFUSION REACTIONS, EMBRYO-FETAL TOXICITY, and PULMONARY TOXICITY

See full prescribing information for complete boxed warning

Cardiomyopathy: trastuzumab products can result in subclinical and clinical cardiac failure manifesting as CHF, and decreased LVEF, with greatest risk when administered concurrently with anthracyclines. Evaluate cardiac function prior to and during treatment. Discontinue Ontruzant for cardiomyopathy. (2.5, 5.1)

Infusion Reactions, Pulmonary Toxicity: Discontinue Ontruzant for anaphylaxis, angioedema, interstitial pneumonitis, or acute respiratory distress syndrome. (5.2, 5.4)

Embryo-Fetal Toxicity: Exposure to trastuzumab products during pregnancy can result in oligohydramnios, in some cases complicated by pulmonary hypoplasia and neonatal death. Advise patients of these risks and the need for effective contraception. (5.3, 8.1, 8.3)

RECENT MAJOR CHANGES

Dosage and Administration, Evaluation and Testing Before Initiating Ontruzant (2.1) | 02/2025

1 INDICATIONS AND USAGE

Ontruzant is a HER2/neu receptor antagonist indicated in adults for:

- The treatment of HER2-overexpressing breast cancer. (1.1, 1.2)
- The treatment of HER2-overexpressing metastatic gastric or gastroesophageal junction adenocarcinoma. (1.3)

Select patients for therapy based on an FDA-approved companion diagnostic for a trastuzumab product (1, 2.2).

2 DOSAGE AND ADMINISTRATION

For intravenous (IV) infusion only. Do not administer as an IV push or bolus. Ontruzant has different dosage and administration instructions than subcutaneous trastuzumab products. (2.3)

Do not substitute Ontruzant (trastuzumab-dttb) for or with ado-trastuzumab emtansine or fam-trastuzumab deruxtecan. (2.3)

Perform HER2 testing using FDA-approved tests by laboratories with demonstrated proficiency. (1, 2.2)

Adjuvant Treatment of HER2-Overexpressing Breast Cancer (2.2)

Administer at either:

- Initial dose of 4 mg/kg over 90 minute IV infusion, then 2 mg/kg over 30 minute IV infusion weekly for 12 weeks (with paclitaxel or docetaxel) or 18 weeks (with docetaxel and carboplatin). One week after the last weekly dose of Ontruzant, administer 6 mg/kg as an IV infusion over 30 to 90 minutes every three weeks to complete a total of 52 weeks of therapy, or
- Initial dose of 8 mg/kg over 90 minutes IV infusion, then 6 mg/kg over 30 to 90 minutes IV infusion every three weeks for 52 weeks.

Metastatic HER2-Overexpressing Breast Cancer (2.3)

- Initial dose of 4 mg/kg as a 90 minute IV infusion followed by subsequent weekly doses of 2 mg/kg as 30 minute IV infusions.

Metastatic HER2-Overexpressing Gastric Cancer (2.3)

- Initial dose of 8 mg/kg over 90 minutes IV infusion, followed by 6 mg/kg over 30 to 90 minutes IV infusion every 3 weeks.

3 DOSAGE FORMS AND STRENGTHS

- For Injection: 150 mg lyophilized powder in a single-dose vial for reconstitution. (3)
- For Injection: 420 mg lyophilized powder in a multiple-dose vial for reconstitution. (3)

4 CONTRAINDICATIONS

- None. (4)

5 WARNINGS AND PRECAUTIONS

- Exacerbation of Chemotherapy-Induced Neutropenia. (5.5, 6.1)

6 ADVERSE REACTIONS

Adjuvant Breast Cancer

- Most common adverse reactions (≥ 5%) are headache, diarrhea, nausea, and chills. (6.1)

Metastatic Breast Cancer

- Most common adverse reactions (≥ 10%) are fever, chills, headache, infection, congestive heart failure, insomnia, cough, and rash. (6.1)

Metastatic Gastric Cancer

- Most common adverse reactions (≥ 10%) are neutropenia, diarrhea, fatigue, anemia, stomatitis, weight loss, upper respiratory tract infections, fever, thrombocytopenia, mucosal inflammation, nasopharyngitis, and dysgeusia. (6.1)

To report SUSPECTED ADVERSE REACTIONS, contact Organon LLC, a subsidiary of Organon & Co., at 1-844-674-3200 or FDA at 1-800-FDA-1088 or www.fda.gov/medwatch.

8 USE IN SPECIFIC POPULATIONS

Females and Males of Reproductive Potential: Verify the pregnancy status of females prior to initiation of Ontruzant (8.3).

FULL PRESCRIBING INFORMATION

WARNING: CARDIOMYOPATHY, INFUSION REACTIONS, EMBRYO-FETAL TOXICITY, and PULMONARY TOXICITY

Cardiomyopathy

Administration of trastuzumab products can result in sub-clinical and clinical cardiac failure. The incidence and severity was highest in patients receiving trastuzumab with anthracycline-containing chemotherapy regimens.
Evaluate left ventricular function in all patients prior to and during treatment with Ontruzant. Discontinue Ontruzant treatment in patients receiving adjuvant therapy and withhold Ontruzant in patients with metastatic disease for clinically significant decrease in left ventricular function [see Dosage and Administration (2.5) and Warnings and Precautions (5.1)].

Infusion Reactions; Pulmonary Toxicity

Administration of trastuzumab products can result in serious and fatal infusion reactions and pulmonary toxicity. Symptoms usually occur during or within 24 hours of administration of trastuzumab products. Interrupt Ontruzant infusion for dyspnea or clinically significant hypotension. Monitor patients until symptoms completely resolve. Discontinue Ontruzant for anaphylaxis, angioedema, interstitial pneumonitis, or acute respiratory distress syndrome [see Warnings and Precautions (5.2, 5.4)].

Embryo-Fetal Toxicity

Exposure to trastuzumab products during pregnancy can result in oligohydramnios and oligohydramnios sequence manifesting as pulmonary hypoplasia, skeletal abnormalities, and neonatal death. Advise patients of these risks and the need for effective contraception [see Warnings and Precautions (5.3) and Use in Specific Populations (8.1, 8.3)].

1 INDICATIONS AND USAGE

1.1 Adjuvant Breast Cancer

Ontruzant is indicated in adults for adjuvant treatment of HER2 overexpressing node positive or node negative (ER/PR negative or with one high risk feature [see Clinical Studies (14.1)]) breast cancer

- as part of a treatment regimen consisting of doxorubicin, cyclophosphamide, and either paclitaxel or docetaxel
- as part of a treatment regimen with docetaxel and carboplatin
- as a single agent following multi-modality anthracycline based therapy.

Select patients for therapy based on an FDA-approved companion diagnostic for a trastuzumab product [see Dosage and Administration (2.2)].

1.2 Metastatic Breast Cancer

Ontruzant is indicated in adults:

- In combination with paclitaxel for first-line treatment of HER2-overexpressing metastatic breast cancer
- As a single agent for treatment of HER2-overexpressing breast cancer in patients who have received one or more chemotherapy regimens for metastatic disease.

Select patients for therapy based on an FDA-approved companion diagnostic for a trastuzumab product [see Dosage and Administration (2.2)].

1.3 Metastatic Gastric Cancer

Ontruzant is indicated in adults, in combination with cisplatin and capecitabine or 5-fluorouracil, for the treatment of patients with HER2-overexpressing metastatic gastric or gastroesophageal junction adenocarcinoma who have not received prior treatment for metastatic disease.

Select patients for therapy based on an FDA-approved companion diagnostic for a trastuzumab product [see Dosage and Administration (2.2)].

2 DOSAGE AND ADMINISTRATION

2.1 Evaluation and Testing Before Initiating Ontruzant

Assess left ventricular ejection fraction (LVEF) prior to initiation of Ontruzant and at regular intervals during treatment. [see Boxed Warning, Dosage and Administration (2.5), Warnings and Precautions (5.1)].

Verify the pregnancy status of females of reproductive potential prior to the initiation of Ontruzant [see Warnings and Precautions (5.3), Use in Specific Populations (8.1, 8.3)].

2.2 Patient Selection

Select patients based on HER2 protein overexpression or HER2 gene amplification in tumor specimens [see Indications and Usage (1) and Clinical Studies (14)]. Assessment of HER2 protein overexpression and HER2 gene amplification should be performed using FDA-approved tests specific for breast or gastric cancers by laboratories with demonstrated proficiency. Information on the FDA-approved tests for the detection of HER2 protein overexpression and HER2 gene amplification is available at: http://www.fda.gov/CompanionDiagnostics.

Assessment of HER2 protein overexpression and HER2 gene amplification in metastatic gastric cancer should be performed using FDA-approved tests specifically for gastric cancers due to differences in gastric vs. breast histopathology, including incomplete membrane staining and more frequent heterogeneous expression of HER2 seen in gastric cancers.

Improper assay performance, including use of suboptimally fixed tissue, failure to utilize specified reagents, deviation from specific assay instructions, and failure to include appropriate controls for assay validation, can lead to unreliable results.

2.3 Recommended Dosage

- Ontruzant is for intravenous infusion only. Do not administer as an intravenous push or bolus.
- Ontruzant has different dosage and administration instructions than subcutaneous trastuzumab products.
- Do not mix Ontruzant with other drugs.
- Do not substitute Ontruzant (trastuzumab-dttb) for or with ado-trastuzumab emtansine or fam-trastuzumab deruxtecan.

Adjuvant Treatment of Breast Cancer:

Administer according to one of the following doses and schedules for a total of 52 weeks of Ontruzant therapy:

During and following paclitaxel, docetaxel, or docetaxel and carboplatin:

- Initial dose of 4 mg/kg as an intravenous infusion over 90 minutes then at 2 mg/kg as an intravenous infusion over 30 minutes weekly during chemotherapy for the first 12 weeks (paclitaxel or docetaxel) or 18 weeks (docetaxel and carboplatin).
- One week following the last weekly dose of Ontruzant, administer Ontruzant at 6 mg/kg as an intravenous infusion over 30 to 90 minutes every three weeks.

As a single agent within three weeks following completion of multi-modality, anthracycline-based chemotherapy regimens:

- Initial dose at 8 mg/kg as an intravenous infusion over 90 minutes
- Subsequent doses at 6 mg/kg as an intravenous infusion over 30 to 90 minutes every three weeks
- Extending adjuvant treatment beyond one year is not recommended [see Adverse Reactions (6.1)].

Metastatic Breast Cancer:

- Administer Ontruzant, alone or in combination with paclitaxel, at an initial dose of 4 mg/kg as a 90-minute intravenous infusion followed by subsequent once weekly doses of 2 mg/kg as 30-minute intravenous infusions until disease progression.

Metastatic Gastric Cancer:

- Administer Ontruzant at an initial dose of 8 mg/kg as a 90-minute intravenous infusion followed by subsequent doses of 6 mg/kg as an intravenous infusion over 30 to 90 minutes every three weeks until disease progression.

2.4 Important Dosing Considerations

Missed Dose

If the patient has missed a dose of Ontruzant by one week or less, then the usual maintenance dose (weekly schedule: 2 mg/kg; once every three weeks schedule: 6 mg/kg) should be administered as soon as possible. Do not wait until the next planned cycle. Subsequent Ontruzant maintenance doses should be administered 7 days or 21 days later according to the weekly or once every three weeks schedules, respectively.

If the patient has missed a dose of Ontruzant by more than one week, a re-loading dose of Ontruzant should be administered over approximately 90 minutes (weekly schedule: 4 mg/kg; once every three weeks schedule: 8 mg/kg) as soon as possible. Subsequent Ontruzant maintenance doses (weekly schedule: 2 mg/kg; three-weekly schedule 6 mg/kg) should be administered 7 days or 21 days later according to the weekly or once every three weeks schedules, respectively.

2.5 Dosage Modifications for Adverse Reactions

Infusion Reactions

[see Boxed Warning, Warnings and Precautions (5.2)]

- Decrease the rate of infusion for mild or moderate infusion reactions
- Interrupt the infusion in patients with dyspnea or clinically significant hypotension
- Discontinue Ontruzant for severe or life-threatening infusion reactions.

Cardiomyopathy

[see Boxed Warning, Warnings and Precautions (5.1)]

Assess left ventricular ejection fraction (LVEF) prior to initiation of Ontruzant and at regular intervals during treatment. Withhold Ontruzant dosing for at least 4 weeks for either of the following:

- ≥ 16% absolute decrease in LVEF from pre-treatment values
- LVEF below institutional limits of normal and ≥ 10% absolute decrease in LVEF from pretreatment values.

Ontruzant may be resumed if, within 4 to 8 weeks, the LVEF returns to normal limits and the absolute decrease from baseline is ≤15%.

Permanently discontinue Ontruzant for a persistent (> 8 weeks) LVEF decline or for suspension of Ontruzant dosing on more than 3 occasions for cardiomyopathy.

2.6 Preparation Instructions

To prevent medication errors, it is important to check the vial labels to ensure that the drug being prepared and administered is Ontruzant (trastuzumab-dttb) and not ado-trastuzumab emtansine or fam-trastuzumab deruxtecan.

420 mg Multiple-dose vial

Reconstitution: Reconstitute each 420 mg vial of Ontruzant with 20 mL of Bacteriostatic Water for Injection (BWFI), USP, containing 1.1% benzyl alcohol as a preservative to yield a multiple-dose solution containing 21 mg/mL trastuzumab-dttb that delivers 20 mL (420 mg trastuzumab-dttb). In patients with known hypersensitivity to benzyl alcohol, reconstitute with 20 mL of Sterile Water for Injection (SWFI) without preservative to yield a one-time use solution.

Use appropriate aseptic technique when performing the following reconstitution steps:

- Using a sterile syringe, slowly inject the 20 mL of diluent into the vial containing the lyophilized powder of Ontruzant, which has a cake-like appearance. The stream of diluent should be directed into the cake. The reconstituted vial yields a solution for multiple-dose use, containing 21 mg/mL trastuzumab-dttb.
- Swirl the vial gently to aid reconstitution. DO NOT SHAKE.
- Slight foaming of the product may be present upon reconstitution. Allow the vial to stand undisturbed for approximately 5 minutes.
- Parenteral drug products should be inspected visually for particulate matter and discoloration prior to administration, whenever solution and container permit. Inspect visually for particulates and discoloration. The solution should be free of visible particulates, clear to slightly opalescent and colorless to pale yellow.
- Store reconstituted Ontruzant in the refrigerator at 2° to 8°C (36° to 46°F); discard unused Ontruzant after 28 days. If Ontruzant is reconstituted with SWFI without preservative, use immediately and discard any unused portion. Do not freeze.

Dilution:

- Determine the dose (mg) of Ontruzant [see Dosage and Administration (2.3)].
- Calculate the volume of the 21 mg/mL reconstituted Ontruzant solution needed, withdraw this amount from the vial and add it to an infusion bag containing 250 mL of 0.9% Sodium Chloride Injection, USP. DO NOT USE DEXTROSE (5%) SOLUTION.
- Gently invert the bag to mix the solution.
- The solution of Ontruzant for infusion diluted in polyvinylchloride or polyethylene bags containing 0.9% Sodium Chloride Injection, USP, should be stored at 2° to 8°C (36° to 46°F) for no more than 24 hours prior to use. This storage time is additional to the time allowed for the reconstituted vials. Do not freeze.

150 mg Single-dose vial

Reconstitution: Reconstitute each 150 mg vial of Ontruzant with 7.4 mL of Sterile Water for Injection (SWFI) (not supplied) to yield a single-dose solution containing 21 mg/mL trastuzumab-dttb that delivers 7.15 mL (150 mg trastuzumab-dttb).

Use appropriate aseptic technique when performing the following reconstitution steps:

- Using a sterile syringe, slowly inject 7.4 mL of SWFI (not supplied) into the vial containing the lyophilized powder of Ontruzant, which has a cake-like appearance. The stream of diluent should be directed into the cake. The reconstituted vial yields a solution containing 21 mg/mL trastuzumab-dttb.
- Gently swirl and invert the vial to aid reconstitution. DO NOT SHAKE.
- Slight foaming of the product may be present upon reconstitution. Allow the vial to stand undisturbed for approximately 5 minutes.
- Parenteral drug products should be inspected visually for particulate matter and discoloration prior to administration, whenever solution and container permit. Inspect visually for particulates and discoloration. The solution should be free of visible particulates, clear to slightly opalescent and colorless to pale yellow.
- Use the Ontruzant solution immediately following reconstitution with SWFI, as it contains no preservative and is intended for one-time use only. If not used immediately, store the reconstituted Ontruzant solution for up to 24 hours at 2° to 8°C (36° to 46°F); discard any unused Ontruzant after 24 hours. Do not freeze.

Dilution:

- Determine the dose (mg) of Ontruzant [see Dosage and Administration (2.3)].
- Calculate the volume of the 21 mg/mL reconstituted Ontruzant solution needed
- Withdraw this amount from the vial and add it to an infusion bag containing 250 mL of 0.9% Sodium Chloride Injection, USP. DO NOT USE DEXTROSE (5%) SOLUTION.
- Gently invert the bag to mix the solution.
- The solution of Ontruzant for infusion diluted in polyvinylchloride or polyethylene bags containing 0.9% Sodium Chloride Injection, USP, should be stored at 2° to 8°C (36° to 46°F) for no more than 24 hours prior to use. Discard after 24 hours. This storage time is additional to the time allowed for the reconstituted vials. Do not freeze.

3 DOSAGE FORMS AND STRENGTHS

- For injection: 150 mg of Ontruzant as a white to pale yellow, preservative-free lyophilized powder in a single-dose vial.
- For injection: 420 mg of Ontruzant as a white to pale yellow, preservative-free lyophilized powder in a multiple-dose vial.

4 CONTRAINDICATIONS

None.

5 WARNINGS AND PRECAUTIONS

5.1 Cardiomyopathy

Trastuzumab products can cause left ventricular cardiac dysfunction, arrhythmias, hypertension, disabling cardiac failure, cardiomyopathy, and cardiac death [see Boxed Warning: Cardiomyopathy]. Trastuzumab products can also cause asymptomatic decline in left ventricular ejection fraction (LVEF).

There is a 4 to 6 fold increase in the incidence of symptomatic myocardial dysfunction among patients receiving trastuzumab products as a single agent or in combination therapy compared with those not receiving trastuzumab products. The highest absolute incidence occurs when a trastuzumab product is administered with an anthracycline.

Withhold Ontruzant for ≥ 16% absolute decrease in LVEF from pre-treatment values or an LVEF value below institutional limits of normal and ≥ 10% absolute decrease in LVEF from pretreatment values [see Dosage and Administration (2.5)]. The safety of continuation or resumption of trastuzumab products in patients with trastuzumab product-induced left ventricular cardiac dysfunction has not been studied.

Patients who receive anthracycline after stopping trastuzumab products may also be at increased risk of cardiac dysfunction [see Drug Interactions (7) and Clinical Pharmacology (12.3)].

Cardiac Monitoring: Conduct thorough cardiac assessment, including history, physical examination, and determination of LVEF by echocardiogram or MUGA scan. The following schedule is recommended:

- Baseline LVEF measurement immediately prior to initiation of Ontruzant
- LVEF measurements every 3 months during and upon completion of Ontruzant
- Repeat LVEF measurement at 4 week intervals if Ontruzant is withheld for significant left ventricular cardiac dysfunction [see Dosage and Administration (2.5)]
- LVEF measurements every 6 months for at least 2 years following completion of Ontruzant as a component of adjuvant therapy.

In NSABPB31, 15% (158/1031) of patients discontinued trastuzumab due to clinical evidence of myocardial dysfunction or significant decline in LVEF after a median follow-up duration of 8.7 years in the AC-TH (anthracycline, cyclophosphamide, paclitaxel, and trastuzumab) arm. In HERA (one-year trastuzumab treatment), the number of patients who discontinued trastuzumab due to cardiac toxicity at 12.6 months median duration of follow-up was 2.6% (44/1678). In BCIRG006, a total of 2.9% (31/1056) of patients in the TCH (docetaxel, carboplatin, trastuzumab) arm (1.5% during the chemotherapy phase and 1.4% during the monotherapy phase) and 5.7% (61/1068) of patients in the AC-TH arm (1.5% during the chemotherapy phase and 4.2% during the monotherapy phase) discontinued trastuzumab due to cardiac toxicity.

Among 64 patients receiving adjuvant chemotherapy (NSABP B31 and NCCTG N9831) who developed congestive heart failure, one patient died of cardiomyopathy, one patient died suddenly without documented etiology, and 33 patients were receiving cardiac medication at last follow-up. Approximately 24% of the surviving patients had recovery to a normal LVEF (defined as ≥ 50%) and no symptoms on continuing medical management at the time of last follow-up. Incidence of congestive heart failure (CHF) is presented in Table 1. The safety of continuation or resumption of trastuzumab products in patients with trastuzumab product-induced left ventricular cardiac dysfunction has not been studied.

Table 1 Incidence of Congestive Heart Failure in Adjuvant Breast Cancer Studies
 |  | Incidence of Congestive Heart Failure % (n)
Study | Regimen | Trastuzumab | Control
NSABP B31 & NCCTG N9831 [Median follow-up duration for NSABP B31 & NCCTG N9831 combined was 8.3 years in the AC → paclitaxel+trastuzumab arm.] | AC [Anthracycline (doxorubicin) and cyclophosphamide.] → Paclitaxel + Trastuzumab | 3.2% (64/2000) [Includes 1 patient with fatal cardiomyopathy and 1 patient with sudden death without documented etiology.] | 1.3% (21/1655)
HERA [Includes NYHA II-IV and cardiac death at 12.6 months median duration of follow-up in the one-year trastuzumab arm.] | Chemotherapy → Trastuzumab | 2% (30/1678) | 0.3% (5/1708)
BCIRG006 | AC → Docetaxel + Trastuzumab | 2% (20/1068) | 0.3% (3/1050)
BCIRG006 | Docetaxel + Carboplatin + Trastuzumab | 0.4% (4/1056) | 0.3% (3/1050)

In HERA (one-year trastuzumab treatment), at a median follow-up duration of 8 years, the incidence of severe CHF (NYHA III & IV) was 0.8%, and the rate of mild symptomatic and asymptomatic left ventricular dysfunction was 4.6%.

Table 2 Incidence of Cardiac Dysfunction [Congestive heart failure or significant asymptomatic decrease in LVEF.] in Metastatic Breast Cancer Studies
Study | Event | Incidence
Study | Event | NYHA I-IV |  | NYHA III−IV
Study | Event | Trastuzumab | Control | Trastuzumab | Control
H0648g (AC) [Anthracycline (doxorubicin or epirubicin) and cyclophosphamide.] | Cardiac Dysfunction | 28% | 7% | 19% | 3%
H0648g (paclitaxel) | Cardiac Dysfunction | 11% | 1% | 4% | 1%
H0649g | Cardiac Dysfunction [Includes 1 patient with fatal cardiomyopathy.] | 7% | N/A | 5% | N/A

In BCIRG006, the incidence of NCI-CTC Grade 3/4 cardiac ischemia/infarction was higher in the trastuzumab containing regimens (AC-TH: 0.3% (3/1068) and TCH: 0.2% (2/1056)) as compared to none in AC-T.

5.2 Infusion Reactions

Infusion reactions consist of a symptom complex characterized by fever and chills, and on occasion included nausea, vomiting, pain (in some cases at tumor sites), headache, dizziness, dyspnea, hypotension, rash, and asthenia [see Adverse Reactions (6.1)].

In post-marketing reports, serious and fatal infusion reactions have been reported. Severe reactions, which include bronchospasm, anaphylaxis, angioedema, hypoxia, and severe hypotension, were usually reported during or immediately following the initial infusion. However, the onset and clinical course were variable, including progressive worsening, initial improvement followed by clinical deterioration, or delayed post-infusion events with rapid clinical deterioration. For fatal events, death occurred within hours to days following a serious infusion reaction.

Interrupt Ontruzant infusion in all patients experiencing dyspnea, clinically significant hypotension, and intervention of medical therapy administered (which may include epinephrine, corticosteroids, diphenhydramine, bronchodilators, and oxygen). Patients should be evaluated and carefully monitored until complete resolution of signs and symptoms. Permanent discontinuation should be strongly considered in all patients with severe infusion reactions.

There are no data regarding the most appropriate method of identification of patients who may safely be retreated with trastuzumab products after experiencing a severe infusion reaction. Prior to resumption of trastuzumab infusion, the majority of patients who experienced a severe infusion reaction were pre-medicated with antihistamines and/or corticosteroids. While some patients tolerated trastuzumab infusions, others had recurrent severe infusion reactions despite pre-medications.

5.3 Embryo-Fetal Toxicity

Trastuzumab products can cause fetal harm when administered to a pregnant woman. In post-marketing reports, use of trastuzumab during pregnancy resulted in cases of oligohydramnios and oligohydramnios sequence manifesting as pulmonary hypoplasia, skeletal abnormalities, and neonatal death.

Verify the pregnancy status of females of reproductive potential prior to the initiation of Ontruzant. Advise pregnant women and females of reproductive potential that exposure to Ontruzant during pregnancy or within 7 months prior to conception can result in fetal harm. Advise females of reproductive potential to use effective contraception during treatment and for 7 months following the last dose of Ontruzant [see Use in Specific Populations (8.1, 8.3) and Clinical Pharmacology (12.3)].

5.4 Pulmonary Toxicity

Trastuzumab product use can result in serious and fatal pulmonary toxicity. Pulmonary toxicity includes dyspnea, interstitial pneumonitis, pulmonary infiltrates, pleural effusions, non-cardiogenic pulmonary edema, pulmonary insufficiency and hypoxia, acute respiratory distress syndrome, and pulmonary fibrosis. Such events can occur as sequelae of infusion reactions [see Warnings and Precautions (5.2)]. Patients with symptomatic intrinsic lung disease or with extensive tumor involvement of the lungs, resulting in dyspnea at rest, appear to have more severe toxicity.

5.5 Exacerbation of Chemotherapy-Induced Neutropenia

In randomized, controlled clinical trials, the per-patient incidences of NCI-CTC Grade 3 to 4 neutropenia and of febrile neutropenia were higher in patients receiving trastuzumab in combination with myelosuppressive chemotherapy as compared to those who received chemotherapy alone. The incidence of septic death was similar among patients who received trastuzumab and those who did not [see Adverse Reactions (6.1)].

6 ADVERSE REACTIONS

The following adverse reactions are discussed in greater detail in other sections of the label:

- Cardiomyopathy [see Warnings and Precautions (5.1)]
- Infusion Reactions [see Warnings and Precautions (5.2)]
- Embryo-Fetal Toxicity [see Warnings and Precautions (5.3)]
- Pulmonary Toxicity [see Warnings and Precautions (5.4)]
- Exacerbation of Chemotherapy-induced Neutropenia [see Warnings and Precautions (5.5)]

6.1 Clinical Trials Experience

Because clinical trials are conducted under widely varying conditions, adverse reaction rates observed in the clinical trials of a drug cannot be directly compared to rates in the clinical trials of another drug and may not reflect the rates observed in practice.

The most common adverse reactions in patients receiving trastuzumab products in the adjuvant and metastatic breast cancer setting are fever, nausea, vomiting, infusion reactions, diarrhea, infections, increased cough, headache, fatigue, dyspnea, rash, neutropenia, anemia, and myalgia. Adverse reactions requiring interruption or discontinuation of trastuzumab product treatment include CHF, significant decline in left ventricular cardiac function, severe infusion reactions, and pulmonary toxicity [see Dosage and Administration (2.5)].

In the metastatic gastric cancer setting, the most common adverse reactions (≥ 10%) that were increased (≥ 5% difference) in the trastuzumab arm as compared to the chemotherapy alone arm were neutropenia, diarrhea, fatigue, anemia, stomatitis, weight loss, upper respiratory tract infections, fever, thrombocytopenia, mucosal inflammation, nasopharyngitis, and dysgeusia. The most common adverse reactions which resulted in discontinuation of treatment on the trastuzumab-containing arm in the absence of disease progression were infection, diarrhea, and febrile neutropenia.

Adjuvant Breast Cancer

The information below reflects exposure to one-year trastuzumab therapy across three randomized, open-label studies, NSABP B31, NCCTG N9831, and HERA, with (n = 3678) or without (n = 3363) trastuzumab in the adjuvant treatment of breast cancer.

HERA

Table 3 reflects exposure to trastuzumab in 1678 patients in HERA; the median treatment duration was 51 weeks and median number of infusions was 18 [see Clinical Studies (14.1)].

Table 3 Adverse Reactions (≥1%) in HERA (All Grades) [The incidence of Grade 3 or higher adverse reactions was <1% in both arms for each listed term.]
Adverse Reactions | Trastuzumab (n = 1678) % | Observation (n = 1708) %
Nervous System
Headache | 10 | 3
Paresthesia | 2 | 0.6
Musculoskeletal
Arthralgia | 8 | 6
Back pain | 5 | 3
Myalgia | 4 | 1
Bone pain | 3 | 2
Muscle spasm | 3 | 0.2
Infections
Nasopharyngitis | 8 | 3
Urinary tract infection | 3 | 0.8
Gastrointestinal
Diarrhea | 7 | 1
Nausea | 6 | 1
Vomiting | 3.5 | 0.6
Constipation | 2 | 1
Dyspepsia | 2 | 0.5
Upper abdominal pain | 2 | 1
General
Pyrexia | 6 | 0.4
Peripheral edema | 5 | 2
Chills | 5 | 0
Asthenia | 4.5 | 2
Influenza-like illness | 2 | 0.2
Respiratory Thoracic Mediastinal
Cough | 5 | 2
Influenza | 4 | 0.5
Dyspnea | 3 | 2
URI | 3 | 1
Rhinitis | 2 | 0.4
Pharyngolaryngeal pain | 2 | 0.5
Sinusitis | 2 | 0.3
Epistaxis | 2 | 0.06
Cardiac
Hypertension | 4 | 2
Dizziness | 4 | 2
Ejection fraction decreased | 3.5 | 0.6
Palpitations | 3 | 0.7
Cardiac arrhythmias [Higher level grouping term.] | 3 | 1
Cardiac failure (congestive) | 2 | 0.3
Skin & Subcutaneous Tissue
Rash | 4 | 0.6
Nail disorders | 2 | 0
Pruritus | 2 | 0.6

Clinically relevant adverse reactions in < 1% of patients who received trastuzumab in HERA included hypersensitivity (0.6%), cardiac failure (0.5%), cardiac disorder (0.3%), interstitial pneumonitis (0.2%), pulmonary hypertension (0.2%), ventricular disorder (0.2%), autoimmune thyroiditis (0.3%), and sudden death (0.06%).

Adjuvant Treatment of Breast Cancer with Trastuzumab Beyond One Year

Extending adjuvant treatment beyond one year is not recommended [see Dosage and Administration (2.3)]. In HERA, a comparison of trastuzumab administered once every 3 weeks for two years versus one year was performed. The rate of asymptomatic cardiac dysfunction was increased in the 2-year trastuzumab compared to the 1-year trastuzumab treatment arm (8.1% versus 4.6%, respectively). More patients experienced at least one adverse reaction of Grade 3 or higher in the 2-year trastuzumab treatment arm (20.4%) compared with the one-year trastuzumab treatment arm (16.3%).

NSABP B31 and NCCTG N9831

The safety data from NSABP B31 and NCCTG N9831 were obtained from 3655 patients, of whom 2000 received trastuzumab; the median treatment duration was 51 weeks [see Clinical Studies (14.1)].

In NSABPB31, only Grade 3 to 5 adverse events, treatment-related Grade 2 events, and Grade 2−5 dyspnea were collected during and for up to 3 months following protocol-specified treatment. The following non-cardiac adverse reactions of Grade 2 to 5 occurred at an incidence of at least 2% greater among patients receiving trastuzumab plus chemotherapy as compared to chemotherapy alone: fatigue (29.5% vs. 22.4%), infection (24.0% vs. 12.8%), hot flashes (17.1% vs. 15.0%), anemia (12.3% vs. 6.7%), dyspnea (11.8% vs. 4.6%), rash/desquamation (10.9% vs. 7.6%), leukopenia (10.5% vs. 8.4%), neutropenia (6.4% vs. 4.3%), headache (6.2% vs. 3.8%), pain (5.5% vs. 3.0%), edema (4.7% vs. 2.7%), and insomnia (4.3% vs. 1.5%). The majority of these events were Grade 2 in severity.

In NCCTG N9831, data collection was limited to the following investigator-attributed treatment-related adverse reactions: NCI-CTC Grade 4 and 5 hematologic toxicities, Grade 3 to 5 non-hematologic toxicities, selected Grade 2 to 5 toxicities associated with taxanes (myalgia, arthralgias, nail changes, motor neuropathy, and sensory neuropathy) and Grade 1 to 5 cardiac toxicities occurring during chemotherapy and/or trastuzumab treatment. The following non-cardiac adverse reactions of Grade 2 to 5 occurred at an incidence of at least 2% greater among patients receiving trastuzumab plus chemotherapy as compared to chemotherapy alone: arthralgia (12.2% vs. 9.1%), nail changes (11.5% vs. 6.8%), dyspnea (2.4% vs. 0.2%), and diarrhea (2.2% vs. 0%). The majority of these events were Grade 2 in severity.

BCIRG006

Safety data from BCIRG006 reflect exposure to trastuzumab as part of an adjuvant treatment regimen from 2124 patients receiving at least one dose of study treatment [AC-TH: n = 1068; TCH: n = 1056]. The overall median treatment duration was 54 weeks in both the AC-TH and TCH arms. The median number of infusions was 26 in the AC-TH arm and 30 in the TCH arm, including weekly infusions during the chemotherapy phase and every three week dosing in the monotherapy period [see Clinical Studies (14.1)]. In BCIRG006, the toxicity profile was similar to that reported in NSABP B31, NCCTG N9831, and HERA with the exception of a lower incidence of CHF in the TCH arm.

Metastatic Breast Cancer Studies

The safety of trastuzumab was evaluated in one randomized, open-label study (H0648g) of chemotherapy with (n = 235) or without (n = 234) intravenous trastuzumab in patients with metastatic breast cancerand in one single-arm study (H0649g); in patients with metastatic breast cancer (n=222) [see Clinical Studies (14.1)]. Patients received 4 mg/kg initial dose of trastuzumab followed by 2 mg/kg weekly. In H0648g, 58% of patients received trastuzumab for ≥ 6 months and 9% received trastuzumab for ≥ 12 months, respectively. In H0649g, 31% of patients received trastuzumab for ≥ 6 months and 16% received trastuzumab for ≥ 12 months, respectively. Table 4 shows the adverse reactions (≥ 5%) in patients from H0648g and H0649g.

Table 4 Adverse Reactions^3 (5%) in the Trastuzumab Arms in H0648g and H0649g
 | Trastuzumab [Data for trastuzumab single agent were from 4 studies, including 213 patients from H0649g .] n = 352 % | Trastuzumab + Paclitaxel n = 91 % | Paclitaxel n = 95 % | Trastuzumab + AC [Anthracycline (doxorubicin or epirubicin) and cyclophosphamide.] n = 143 % | AC n = 135 %
General
Pain | 47 | 61 | 62 | 57 | 42
Asthenia | 42 | 62 | 57 | 54 | 55
Fever | 36 | 49 | 23 | 56 | 34
Chills | 32 | 41 | 4 | 35 | 11
Headache | 26 | 36 | 28 | 44 | 31
Abdominal pain | 22 | 34 | 22 | 23 | 18
Back pain | 22 | 34 | 30 | 27 | 15
Infection | 20 | 47 | 27 | 47 | 31
Flu syndrome | 10 | 12 | 5 | 12 | 6
Accidental injury | 6 | 13 | 3 | 9 | 4
Allergic reaction | 3 | 8 | 2 | 4 | 2
Gastrointestinal
Nausea | 33 | 51 | 9 | 76 | 77
Diarrhea | 25 | 45 | 29 | 45 | 26
Vomiting | 23 | 37 | 28 | 53 | 49
Anorexia | 14 | 24 | 16 | 31 | 26
Nausea and vomiting | 8 | 14 | 11 | 18 | 9
Respiratory
Cough increased | 26 | 41 | 22 | 43 | 29
Dyspnea | 22 | 27 | 26 | 42 | 25
Rhinitis | 14 | 22 | 5 | 22 | 16
Pharyngitis | 12 | 22 | 14 | 30 | 18
Sinusitis | 9 | 21 | 7 | 13 | 6
Skin
Rash | 18 | 38 | 18 | 27 | 17
Herpes simplex | 2 | 12 | 3 | 7 | 9
Acne | 2 | 11 | 3 | 3 | < 1
Nervous
Insomnia | 14 | 25 | 13 | 29 | 15
Dizziness | 13 | 22 | 24 | 24 | 18
Paresthesia | 9 | 48 | 39 | 17 | 11
Depression | 6 | 12 | 13 | 20 | 12
Peripheral neuritis | 2 | 23 | 16 | 2 | 2
Neuropathy | 1 | 13 | 5 | 4 | 4
Metabolic
Peripheral edema | 10 | 22 | 20 | 20 | 17
Edema | 8 | 10 | 8 | 11 | 5
Cardiovascular
Congestive heart failure | 7 | 11 | 1 | 28 | 7
Tachycardia | 5 | 12 | 4 | 10 | 5
Musculoskeletal
Bone pain | 7 | 24 | 18 | 7 | 7
Arthralgia | 6 | 37 | 21 | 8 | 9
Urogenital
Urinary tract infection | 5 | 18 | 14 | 13 | 7
Blood and Lymphatic
Anemia | 4 | 14 | 9 | 36 | 26
Leukopenia | 3 | 24 | 17 | 52 | 34

Metastatic Gastric Cancer

The safety of trastuzumab was evaluated in patients with previously untreated for metastatic gastric or gastroesophageal junction adenocarcinoma in an open label, multi-center trial (ToGA) [see Clinical Studies (14.3)]. Patients were randomized (1:1) to receive trastuzumab in combination with cisplatin and a fluoropyrimidine (FC+H) (n=294) or chemotherapy alone (FC) (n=290) Patients in the trastuzumab plus chemotherapy arm received trastuzumab 8 mg/kg administered on Day 1 (prior to chemotherapy) followed by 6 mg/kg every 21 days until disease progression. Cisplatin was administered at 80 mg/m^2 on Day 1 and the fluoropyrimidine was administered as either capecitabine 1000 mg/m^2 orally twice a day on Days 1 to 14 or 5-fluorouracil 800 mg/m^2/day as a continuous intravenous infusion Days 1 through 5. Chemotherapy was administered for six 21-day cycles. Median duration of trastuzumab treatment was 21 weeks and the median number of trastuzumab infusions administered was eight.

Table 5 Adverse Reactions (All Grades ≥ 5% or Grade 3-4 ≥ 1% between Arms) in ToGA
Adverse Reactions | Trastuzumab + FC (N = 294) (%) |  | FC (N = 290) (%)
Adverse Reactions | All Grades | Grades 3/4 | All Grades | Grades 3/4
Investigations
Neutropenia | 78 | 34 | 73 | 29
Hypokalemia | 28 | 10 | 24 | 6
Anemia | 28 | 12 | 21 | 10
Thrombocytopenia | 16 | 5 | 11 | 3
Blood and Lymphatic System Disorders
Febrile Neutropenia | - | 5 | - | 3
Gastrointestinal Disorders
Diarrhea | 37 | 9 | 28 | 4
Stomatitis | 24 | 1 | 15 | 2
Dysphagia | 6 | 2 | 3 | < 1
General
Fatigue | 35 | 4 | 28 | 2
Fever | 18 | 1 | 12 | 0
Mucosal Inflammation | 13 | 2 | 6 | 1
Chills | 8 | < 1 | 0 | 0
Metabolism and Nutrition Disorders
Weight Decrease | 23 | 2 | 14 | 2
Infections and Infestations
Upper Respiratory Tract Infections | 19 | 0 | 10 | 0
Nasopharyngitis | 13 | 0 | 6 | 0
Renal and Urinary Disorders
Renal Failure and Impairment | 18 | 3 | 15 | 2
Nervous System Disorders
Dysgeusia | 10 | 0 | 5 | 0

The following subsections provide additional detail regarding adverse reactions observed in clinical trials of adjuvant breast cancer, metastatic breast cancer, metastatic gastric cancer, or post-marketing experience.

Cardiomyopathy

Serial measurement of cardiac function (LVEF) was obtained in clinical trials in the adjuvant treatment of breast cancer. In HERA, the median duration of follow-up was 12.6 months (12.4 months in the observation arm; 12.6 months in the 1-year trastuzumab arm); and in NSABP B31 and NCCTG N9831, 7.9 years in the AC-T arm, 8.3 years in the AC-TH arm. Following initiation of trastuzumab therapy, the incidence of new-onset dose-limiting myocardial dysfunction was higher among patients receiving trastuzumab and paclitaxel as compared to those receiving paclitaxel alone in NSABP B31 and NCCTG N9831, and in patients receiving one-year trastuzumab monotherapy compared to observation in HERA (see Table 6, Figures 1 and 2). The incidence of new-onset cardiac dysfunction, as measured by LVEF, remained similar when compared to the analysis performed at a median follow-up of 2.0 years in the AC-TH arm. This analysis showed evidence of reversibility of left ventricular dysfunction, with 64.5% of patients who experienced symptomatic CHF in the AC-TH group being asymptomatic at latest follow-up, and 90.3% having full or partial LVEF recovery.

Table 6 Myocardial Dysfunction (by LVEF) in NSABP B31, NCCTG N9831, HERA, and BCIRG006 [For NSABP B31, NCCTG N9831, and HERA, events are counted from the beginning of trastuzumab treatment. For BCIRG006, events are counted from the date of randomization.]
Study and Arm | LVEF < 50% and Decrease from Baseline |  |  | LVEF Decrease
Study and Arm | LVEF < 50% | ≥ 10% decrease | ≥ 16% decrease | < 20% and ≥ 10% | ≥ 20%
NSABP B31 & NCCTG N9831 [NSABP B31 and NCCTG N9831 regimens: doxorubicin and cyclophosphamide followed by paclitaxel (AC → T) or paclitaxel plus trastuzumab (AC → TH).] , [Median duration of follow-up for NSABP B31 and NCCTG N9831 combined was 8.3 years in the AC → TH arm.]
AC → TH | 23.1% | 18.5% | 11.2% | 37.9% | 8.9%
(n = 1856) | (428) | (344) | (208) | (703) | (166)
AC → T | 11.7% | 7.0% | 3.0% | 22.1% | 3.4%
(n = 1170) | (137) | (82) | (35) | (259) | (40)
HERA [Median follow-up duration of 12.6 months in the one-year trastuzumab treatment arm.]
Trastuzumab | 8.6% | 7.0% | 3.8% | 22.4% | 3.5%
(n = 1678) | (144) | (118) | (64) | (376) | (59)
Observation | 2.7% | 2.0% | 1.2% | 11.9% | 1.2%
(n = 1708) | (46) | (35) | (20) | (204) | (21)
BCIRG006 [BCIRG006 regimens: doxorubicin and cyclophosphamide followed by docetaxel (AC → T) or docetaxel plus trastuzumab (AC → TH); docetaxel and carboplatin plus trastuzumab (TCH).]
TCH | 8.5% | 5.9% | 3.3% | 34.5% | 6.3%
(n = 1056) | (90) | (62) | (35) | (364) | (67)
AC → TH | 17% | 13.3% | 9.8% | 44.3% | 13.2%
(n = 1068) | (182) | (142) | (105) | (473) | (141)
AC → T | 9.5% | 6.6% | 3.3% | 34% | 5.5%
(n = 1050) | (100) | (69) | (35) | (357) | (58)

Figure 1

NSABP B31 and NCCTG N9831: Cumulative Incidence of Time to First LVEF Decline of ≥ 10 Percentage Points from Baseline and to Below 50% with Death as a Competing Risk Event

Time 0 is initiation of paclitaxel or trastuzumab + paclitaxel therapy.

Figure 2

HERA: Cumulative Incidence of Time to First LVEF Decline of ≥ 10 Percentage Points from Baseline and to Below 50% with Death as a Competing Risk Event

Time 0 is the date of randomization.

Figure 3

BCIRG006: Cumulative Incidence of Time to First LVEF Decline of ≥ 10 Percentage Points from Baseline and to Below 50% with Death as a Competing Risk Event

Time 0 is the date of randomization.

The incidence of congestive heart failure among patients in the metastatic breast cancer trials was classified for severity using the New York Heart Association classification system (I−IV, where IV is the most severe level of cardiac failure) (see Table 2). In the metastatic breast cancer trials, the probability of cardiac dysfunction was highest in patients who received trastuzumab concurrently with anthracyclines.

In ToGA, 5.0% of patients in the trastuzumab plus chemotherapy arm compared to 1.1% of patients in the chemotherapy alone arm had LVEF value below 50% with a ≥ 10% absolute decrease in LVEF from pretreatment values.

Infusion Reactions

During the first infusion with trastuzumab, the symptoms most commonly reported were chills and fever, occurring in approximately 40% of patients in clinical trials. Symptoms were treated with acetaminophen, diphenhydramine, and meperidine (with or without reduction in the rate of trastuzumab infusion); permanent discontinuation of trastuzumab for infusion reactions was required in < 1% of patients. Other signs and/or symptoms may include nausea, vomiting, pain (in some cases at tumor sites), rigors, headache, dizziness, dyspnea, hypotension, elevated blood pressure, rash, and asthenia. Infusion reactions occurred in 21% and 35% of patients, and were severe in 1.4% and 9% of patients, on second or subsequent trastuzumab infusions administered as monotherapy or in combination with chemotherapy, respectively. In the post-marketing setting, severe infusion reactions, including hypersensitivity, anaphylaxis, and angioedema have been reported.

Anemia

In randomized controlled clinical trials, the overall incidence of anemia (30% vs. 21% [H0648g]), of selected NCI-CTC Grade 2 to 5 anemia (12.3% vs. 6.7% [NSABPB31]), and of anemia requiring transfusions (0.1% vs. 0 patients [NCCTG N9831]) were increased in patients receiving trastuzumab and chemotherapy compared with those receiving chemotherapy alone. Following the administration of trastuzumab as a single agent (H0649g), the incidence of NCI-CTC Grade 3 anemia was < 1%. In ToGA (metastatic gastric cancer), on the trastuzumab containing arm as compared to the chemotherapy alone arm, the overall incidence of anemia was 28% compared to 21% and of NCI-CTC Grade 3/4 anemia was 12.2% compared to 10.3%.

Neutropenia

In randomized controlled clinical trials in the adjuvant setting, the incidence of selected NCI-CTC Grade 4 to 5 neutropenia (1.7% vs. 0.8% [NCCTG N9831]) and of selected Grade 2 to 5 neutropenia (6.4% vs. 4.3% [NSABPB31]) were increased in patients receiving trastuzumab and chemotherapy compared with those receiving chemotherapy alone. In a randomized, controlled trial in patients with metastatic breast cancer, the incidences of NCI-CTC Grade 3/4 neutropenia (32% vs. 22%) and of febrile neutropenia (23% vs. 17%) were also increased in patients randomized to trastuzumab in combination with myelosuppressive chemotherapy as compared to chemotherapy alone. In ToGA (metastatic gastric cancer) on the trastuzumab containing arm as compared to the chemotherapy alone arm, the incidence of NCI-CTC Grade 3/4 neutropenia was 36.8% compared to 28.9%; febrile neutropenia 5.1% compared to 2.8%.

Infection

The overall incidences of infection (46% vs. 30% [H0648g]), of selected NCI-CTC Grade 2 to 5 infection/febrile neutropenia (24.3% vs. 13.4% [NSABPB31]) and of selected Grade 3 to 5 infection/febrile neutropenia (2.9% vs. 1.4%) [NCCTG N9831]) were higher in patients receiving trastuzumab and chemotherapy compared with those receiving chemotherapy alone. The most common site of infections in the adjuvant setting involved the upper respiratory tract, skin, and urinary tract.

In BCIRG006, the overall incidence of infection was higher with the addition of trastuzumab to AC-T but not to TCH [44% (AC-TH), 37% (TCH), 38% (AC-T)]. The incidences of NCI-CTC Grade 3 to 4 infection were similar [25% (AC-TH), 21% (TCH), 23% (AC-T)] across the three arms.

In a randomized, controlled trial in treatment of metastatic breast cancer, the reported incidence of febrile neutropenia was higher (23% vs. 17%) in patients receiving trastuzumab in combination with myelosuppressive chemotherapy as compared to chemotherapy alone.

Pulmonary Toxicity

Adjuvant Breast Cancer

Among women receiving adjuvant therapy for breast cancer, the incidence of selected NCI-CTC Grade 2 to 5 pulmonary toxicity (14.3% vs. 5.4% [NSABPB31]) and of selected NCI-CTC Grade 3 to 5 pulmonary toxicity and spontaneous reported Grade 2 dyspnea (3.4% vs. 0.9% [NCCTG N9831]) was higher in patients receiving trastuzumab and chemotherapy compared with chemotherapy alone. The most common pulmonary toxicity was dyspnea (NCI-CTC Grade 2 to 5: 11.8% vs. 4.6% [NSABPB31]; NCI-CTC Grade 2 to 5: 2.4% vs. 0.2% [NCCTG N9831]). Pneumonitis/pulmonary infiltrates occurred in 0.7% of patients receiving trastuzumab compared with 0.3% of those receiving chemotherapy alone. Fatal respiratory failure occurred in 3 patients receiving trastuzumab, one as a component of multi-organ system failure, as compared to 1 patient receiving chemotherapy alone.

In HERA, there were 4 cases of interstitial pneumonitis in the one-year trastuzumab treatment arm compared to none in the observation arm at a median follow-up duration of 12.6 months.

Metastatic Breast Cancer

Among women receiving trastuzumab for treatment of metastatic breast cancer, the incidence of pulmonary toxicity was also increased. Pulmonary adverse events have been reported in the post-marketing experience as part of the symptom complex of infusion reactions. Pulmonary events include bronchospasm, hypoxia, dyspnea, pulmonary infiltrates, pleural effusions, non-cardiogenic pulmonary edema, and acute respiratory distress syndrome. For a detailed description, see Warnings and Precautions (5.4).

Thrombosis/Embolism

In 4 randomized, controlled clinical trials, the incidence of thrombotic adverse events was higher in patients receiving trastuzumab and chemotherapy compared to chemotherapy alone in three studies (2.6% vs. 1.5% [NSABPB31], 2.5% and 3.7% vs. 2.2% [BCIRG006] and 2.1% vs. 0% [H0648g]).

Diarrhea

Among women receiving adjuvant therapy for breast cancer, the incidence of NCI-CTC Grade 2 to 5 diarrhea (6.7% vs. 5.4% [NSABPB31]) and of NCI-CTC Grade 3 to 5 diarrhea (2.2% vs. 0% [NCCTG N9831]), and of Grade 1 to 4 diarrhea (7% vs. 1% [HERA; one-year trastuzumab treatment at 12.6 months median duration of follow-up]) were higher in patients receiving trastuzumab as compared to controls. In BCIRG006, the incidence of Grade 3 to 4 diarrhea was higher [5.7% AC-TH, 5.5% TCH vs. 3.0% AC-T] and of Grade 1 to 4 was higher [51% AC-TH, 63% TCH vs. 43% AC-T] among women receiving trastuzumab. Of patients receiving trastuzumab as a single agent for the treatment of metastatic breast cancer, 25% experienced diarrhea. An increased incidence of diarrhea was observed in patients receiving trastuzumab in combination with chemotherapy for treatment of metastatic breast cancer.

Renal Toxicity

In ToGA (metastatic gastric cancer) on the trastuzumab-containing arm as compared to the chemotherapy alone arm the incidence of renal impairment was 18% compared to 14.5%. Severe (Grade 3/4) renal failure was 2.7% on the trastuzumab-containing arm compared to 1.7% on the chemotherapy only arm. Treatment discontinuation for renal insufficiency/failure was 2% on the trastuzumab-containing arm and 0.3% on the chemotherapy only arm.

In the post-marketing setting, rare cases of nephrotic syndrome with pathologic evidence of glomerulopathy have been reported. The time to onset ranged from 4 months to approximately 18 months from initiation of trastuzumab therapy. Pathologic findings included membranous glomerulonephritis, focal glomerulosclerosis, and fibrillary glomerulonephritis. Complications included volume overload and congestive heart failure.

6.2 Post-Marketing Experience

The following adverse reactions have been identified during post-approval use of trastuzumab products. Because these reactions are reported voluntarily from a population of uncertain size, it is not always possible to reliably estimate their frequency or establish a causal relationship to drug exposure.

- Infusion reaction [see Warnings and Precautions (5.2)]
- Oligohydramnios or oligohydramnios sequence, including pulmonary hypoplasia, skeletal abnormalities, and neonatal death [see Warnings and Precautions (5.3)]
- Glomerulopathy [see Adverse Reactions (6.1)]
- Immune thrombocytopenia
- Tumor lysis syndrome (TLS): Cases of possible TLS have been reported in patients treated with trastuzumab products. Patients with significant tumor burden (e.g. bulky metastases) may be at a higher risk. Patients could present with hyperuricemia, hyperphosphatemia, and acute renal failure which may represent possible TLS. Providers should consider additional monitoring and/or treatment as clinically indicated.

7 DRUG INTERACTIONS

Anthracyclines

Patients who receive anthracycline after stopping trastuzumab products may be at increased risk of cardiac dysfunction because of trastuzumab products' estimated long washout period [see Clinical Pharmacology (12.3)]. If possible, avoid anthracycline-based therapy for up to 7 months after stopping trastuzumab products. If anthracyclines are used, closely monitor the patient's cardiac function.

8 USE IN SPECIFIC POPULATIONS

8.1 Pregnancy

Risk Summary

Trastuzumab products can cause fetal harm when administered to a pregnant woman. In post-marketing reports and published literature, use of trastuzumab products during pregnancy resulted in cases of oligohydramnios and of oligohydramnios sequence, manifesting as pulmonary hypoplasia, skeletal abnormalities, and neonatal death (see Data). Apprise the patient of the potential risks to a fetus. There are clinical considerations if a trastuzumab product is used in a pregnant woman or if a patient becomes pregnant within 7 months following the last dose of a trastuzumab product (see Clinical Considerations).

The background risk of major birth defects and miscarriage for the indicated population is unknown. In the U.S. general population, the estimated background risk of major birth defects and miscarriage in clinically recognized pregnancies is 2% to 4% and 15% to 20%, respectively.

Clinical Considerations

Fetal/Neonatal Adverse Reactions

Monitor women who received Ontruzant during pregnancy or within 7 months prior to conception for oligohydramnios. If oligohydramnios occurs, perform fetal/neonatal testing that is appropriate for gestational age and consistent with community standards of care.

Data

Human Data

In post-marketing reports and published literature, use of trastuzumab products during pregnancy resulted in cases of oligohydramnios and of oligohydramnios sequence. Fetal manifestations included pulmonary hypoplasia, skeletal abnormalities, and neonatal death. These case reports described oligohydramnios in pregnant women who received trastuzumab either alone or in combination with chemotherapy. In most reported cases, amniotic fluid index increased after trastuzumab was stopped. In reported cases where trastuzumab therapy was resumed after amniotic index improved, oligohydramnios recurred.

Animal Data

In studies where trastuzumab was administered to pregnant Cynomolgus monkeys during the period of organogenesis at doses up to 25 mg/kg given twice weekly (up to 25 times the recommended weekly human dose of 2 mg/kg), trastuzumab crossed the placental barrier during the early (Gestation Days 20 to 50) and late (Gestation Days 120 to 150) phases of gestation. The resulting concentrations of trastuzumab in fetal serum and amniotic fluid were approximately 33% and 25%, respectively, of those present in the maternal serum but were not associated with adverse developmental effects.

8.2 Lactation

Risk Summary

There is no information regarding the presence of trastuzumab products in human milk, the effects on the breastfed infant, or the effects on milk production. Published data suggest human IgG is present in human milk but does not enter the neonatal and infant circulation in substantial amounts. Trastuzumab was present in the milk of lactating Cynomolgus monkeys but not associated with neonatal toxicity (see Data). Consider the developmental and health benefits of breastfeeding along with the mother's clinical need for Ontruzant treatment and any potential adverse effects on the breastfed child from Ontruzant or from the underlying maternal condition. This consideration should also take into account the trastuzumab product wash out period of 7 months [see Clinical Pharmacology (12.3)].

Data

In lactating cynomolgus monkeys, trastuzumab was present in breast milk at about 0.3% of maternal serum concentrations after pre-(beginning Gestation Day 120) and post-partum (through Post-partum Day 28) doses of 25 mg/kg administered twice weekly (25 times the recommended weekly human dose of 2 mg/kg of trastuzumab products). Infant monkeys with detectable serum levels of trastuzumab did not exhibit any adverse effects on growth or development from birth to 1 month of age.

8.3 Females and Males of Reproductive Potential

Pregnancy Testing

Verify the pregnancy status of females of reproductive potential prior to the initiation of Ontruzant.

Contraception

Females

Trastuzumab products can cause embryo-fetal harm when administered during pregnancy. Advise females of reproductive potential to use effective contraception during treatment with Ontruzant and for 7 months following the last dose of Ontruzant [see Use in Specific Populations (8.1) and Clinical Pharmacology (12.3)].

8.4 Pediatric Use

The safety and effectiveness of Ontruzant in pediatric patients have not been established.

8.5 Geriatric Use

Trastuzumab has been administered to 386 patients who were 65 years of age or over (253 in the adjuvant treatment and 133 in metastatic breast cancer treatment settings). The risk of cardiac dysfunction was increased in geriatric patients as compared to younger patients in both those receiving treatment for metastatic disease in H0648g and H0649g, or adjuvant therapy in NSABP B31 and NCCTG N9831. Limitations in data collection and differences in study design of the 4 studies of trastuzumab in adjuvant treatment of breast cancer preclude a determination of whether the toxicity profile of trastuzumab in older patients is different from younger patients. The reported clinical experience is not adequate to determine whether the efficacy improvements (ORR, TTP, OS, DFS) of trastuzumab treatment in older patients is different from that observed in patients < 65 years of age for metastatic disease and adjuvant treatment.

In ToGA (metastatic gastric cancer), of the 294 patients treated with trastuzumab, 108 (37%) were 65 years of age or older, while 13 (4.4%) were 75 and over. No overall differences in safety or effectiveness were observed.

11 DESCRIPTION

Trastuzumab-dttb is a humanized IgG1 kappa monoclonal antibody that selectively binds with high affinity to the extracellular domain of the human epidermal growth factor receptor 2 protein, HER2. Trastuzumab-dttb is produced by recombinant DNA technology in a mammalian cell (Chinese Hamster Ovary) culture.

Ontruzant (trastuzumab-dttb) for injection is a sterile, white to pale yellow, preservative-free lyophilized powder with a cake-like appearance, for intravenous administration.

Each multiple-dose vial of Ontruzant delivers 420 mg trastuzumab-dttb, 381.4 mg α,α-trehalose dihydrate, 9.4 mg L-histidine HCl monohydrate, 6.1 mg L-histidine, and 1.7 mg polysorbate 20. Reconstitution with 20 mL of the appropriate diluent (BWFI or SWFI) yields a solution containing 21 mg/mL trastuzumab-dttb at a pH of approximately 6. If Ontruzant is reconstituted with SWFI without preservative, the reconstituted solution is considered single-dose.

Each single-dose vial of Ontruzant delivers 150 mg trastuzumab-dttb, 136.2 mg α,α-trehalose dihydrate, 3.4 mg L-histidine HCl monohydrate, 2.2 mg L-histidine, and 0.6 mg polysorbate 20. Reconstitution with 7.4 mL of sterile water for injection (SWFI) yields a solution containing 21 mg/mL trastuzumab-dttb that delivers 7.15 mL (150 mg trastuzumab-dttb), at a pH of approximately 6.

12 CLINICAL PHARMACOLOGY

12.1 Mechanism of Action

The HER2 (or c-erbB2) proto-oncogene encodes a transmembrane receptor protein of 185 kDa, which is structurally related to the epidermal growth factor receptor. Trastuzumab products have been shown, in both in vitro assays and in animals, to inhibit the proliferation of human tumor cells that overexpress HER2.

Trastuzumab products are mediators of antibody-dependent cellular cytotoxicity (ADCC). In vitro, trastuzumab product-mediated ADCC has been shown to be preferentially exerted on HER2 overexpressing cancer cells compared with cancer cells that do not overexpress HER2.

12.2 Pharmacodynamics

Trastuzumab product exposure-response relationships and the time course of pharmacodynamic responses are not fully characterized.

Cardiac Electrophysiology

The effects of trastuzumab on electrocardiographic (ECG) endpoints, including QTc interval duration, were evaluated in patients with HER2 positive solid tumors. Trastuzumab had no clinically relevant effect on the QTc interval duration and there was no apparent relationship between serum trastuzumab concentrations and change in QTcF interval duration in patients with HER2 positive solid tumors.

12.3 Pharmacokinetics

The pharmacokinetics of trastuzumab were evaluated in a pooled population pharmacokinetic (PK) model analysis of 1,582 subjects with primarily breast cancer and metastatic gastric cancer (MGC) receiving intravenous trastuzumab. Total trastuzumab clearance increases with decreasing concentrations due to parallel linear and non-linear elimination pathways.

Although the average trastuzumab exposure was higher following the first cycle in breast cancer patients receiving the once every three week schedule compared to the weekly schedule of trastuzumab, the average steady-state exposure was essentially the same at both dosages. The average trastuzumab exposure following the first cycle and at steady state as well as the time to steady state was higher in breast cancer patients compared to MGC patients at the same dosage; however, the reason for this exposure difference is unknown. Additional predicted trastuzumab exposure and PK parameters following the first trastuzumab cycle and at steady state exposure are described in Tables 7 and 8, respectively.

Population PK based simulations indicate that following discontinuation of trastuzumab, concentrations in at least 95% of breast cancer and MGC patients will decrease to approximately 3% of the population predicted steady-state trough serum concentration (approximately 97% washout) by 7 months [see Warnings and Precautions (5.1) and Use in Specific Populations (8.1, 8.3)].

Table 7 Population Predicted Cycle 1 PK Exposures (Median with 5th to 95th Percentiles) in Breast Cancer and MGC Patients
Schedule | Primary tumor type | N | Cmin (µg/mL) | Cmax (µg/mL) | AUC0-21 days (µg.day/mL)
8 mg/kg + 6 mg/kg q3w | Breast cancer | 1195 | 29.4 (5.8 to 59.5) | 178 (117 to 291) | 1373 (736 to 2245)
8 mg/kg + 6 mg/kg q3w | MGC | 274 | 23.1 (6.1 to 50.3) | 132 (84.2 to 225) | 1109 (588 to 1938)
4 mg/kg + 2 mg/kg qw | Breast cancer | 1195 | 37.7 (12.3 to 70.9) | 88.3 (58 to 144) | 1066 (586 to 1754)

Table 8 Population Predicted Steady State PK Exposures (Median with 5th to 95th Percentiles) in Breast Cancer and MGC Patients
Schedule | Primary tumor type | N | Cmin.ss [Steady-state trough serum concentration of trastuzumab] (µg/mL) | Cmax.ss [Maximum steady-state serum concentration of trastuzumab] (µg/mL) | AUCss, 0-21 days (µg.day/mL) | Time to steady- state (week) | Total CL range at steady-state (L/day)
8 mg/kg + 6 mg/kg q3w | Breast cancer | 1195 | 47.4 (5 to 115) | 179 (107 to 309) | 1794 (673 to 3618) | 12 | 0.173 to 0.283
8 mg/kg + 6 mg/kg q3w | MGC | 274 | 32.9 (6.1 to 88.9) | 131 (72.5 to 251) | 1338 (557 to 2875) | 9 | 0.189 to 0.337
4 mg/kg + 2 mg/kg qw | Breast cancer | 1195 | 66.1 (14.9 to 142) | 109 (51.0 to 209) | 1765 (647 to 3578) | 12 | 0.201 to 0.244

Specific Populations:

Based on a population pharmacokinetic analysis, no clinically significant differences were observed in the pharmacokinetics of trastuzumab based on age (< 65 (n = 1294); ≥ 65 (n = 288)), race (Asian (n = 264); non-Asian (n = 1324)) and renal impairment (mild (creatinine clearance [CLcr] 60 to 90 mL/min) (n = 636) or moderate (CLcr 30 to 60 mL/min) (n = 133)). The pharmacokinetics of trastuzumab products in patients with severe renal impairment, end-stage renal disease with or without hemodialysis, or hepatic impairment is unknown.

Drug Interaction Studies:

There have been no formal drug interaction studies performed with trastuzumab products in humans. Clinically significant interactions between trastuzumab and concomitant medications used in clinical trials have not been observed.

Paclitaxel and doxorubicin: Concentrations of paclitaxel and doxorubicin and their major metabolites (i.e., 6-α hydroxyl-paclitaxel [POH], and doxorubicinol [DOL], respectively) were not altered in the presence of trastuzumab when used as combination therapy in clinical trials. Trastuzumab concentrations were not altered as part of this combination therapy.

Docetaxel and carboplatin: When trastuzumab was administered in combination with docetaxel or carboplatin, neither the plasma concentrations of docetaxel or carboplatin nor the plasma concentrations of trastuzumab were altered.

Cisplatin and capecitabine: In a drug interaction substudy conducted in patients in ToGA, the pharmacokinetics of cisplatin, capecitabine and their metabolites were not altered when administered in combination with trastuzumab.

12.6 Immunogenicity

The observed incidence of anti-drug antibodies is highly dependent on the sensitivity and specificity of the assay. Differences in assay methods preclude meaningful comparisons of the incidence of anti-drug antibodies in the studies described below with the incidence of anti-drug antibodies in other studies, including those of trastuzumab or of other trastuzumab products.

Among 903 women with metastatic breast cancer, human anti human antibody (HAHA) to trastuzumab was detected in one patient using an enzyme linked immunosorbent assay (ELISA). This patient did not experience an allergic reaction. Samples for assessment of HAHA were not collected in studies of adjuvant breast cancer.

The clinical relevance of the development of anti-trastuzumab antibodies after treatment with trastuzumab is not known.

13 NONCLINICAL TOXICOLOGY

13.1 Carcinogenesis, Mutagenesis, Impairment of Fertility

Trastuzumab products have not been tested for carcinogenic potential.

No evidence of mutagenic activity was observed when trastuzumab was tested in the standard Ames bacterial and human peripheral blood lymphocyte mutagenicity assays at concentrations of up to 5000 mcg/mL. In an in vivo micronucleus assay, no evidence of chromosomal damage to mouse bone marrow cells was observed following bolus intravenous doses of up to 118 mg/kg of trastuzumab.

A fertility study was conducted in female cynomolgus monkeys at doses up to 25 times the weekly recommended human dose of 2 mg/kg of trastuzumab and has revealed no evidence of impaired fertility, as measured by menstrual cycle duration and female sex hormone levels.

14 CLINICAL STUDIES

14.1 Adjuvant Breast Cancer

The safety and efficacy of trastuzumab in women receiving adjuvant chemotherapy for HER2 overexpressing breast cancer were evaluated in an integrated analysis of two randomized, open-label, clinical trials (NSABP B31 and NCCTG N9831) with a total of 4063 women at the protocol-specified final overall survival analysis, a third randomized, open-label, clinical trial (HERA) with a total of 3386 women at definitive Disease-Free Survival analysis for one-year trastuzumab treatment versus observation, and a fourth randomized, open-label clinical trial with a total of 3222 patients (BCIRG006).

NSABP B31 and NCCTG N9831:

In NSABP B31 and NCCTG N9831, breast tumor specimens were required to show HER2 overexpression (3+ by IHC) or gene amplification (by FISH). HER2 testing was verified by a central laboratory prior to randomization (NCCTG N9831) or was required to be performed at a reference laboratory (NSABPB31). Patients with a history of active cardiac disease based on symptoms, abnormal electrocardiographic, radiologic, or left ventricular ejection fraction findings or uncontrolled hypertension (diastolic > 100 mm Hg or systolic > 200 mm Hg) were not eligible. Patients were randomized (1:1) to receive doxorubicin and cyclophosphamide followed by paclitaxel (AC → paclitaxel) alone or paclitaxel plus trastuzumab (AC → paclitaxel + trastuzumab). In both trials, patients received four 21-day cycles of doxorubicin 60 mg/m^2 and cyclophosphamide 600 mg/m^2. Paclitaxel was administered either weekly (80 mg/m^2) or every 3 weeks (175 mg/m^2) for a total of 12 weeks in NSABPB31; paclitaxel was administered only by the weekly schedule in NCCTG N9831. Trastuzumab was administered at 4 mg/kg on the day of initiation of paclitaxel and then at a dose of 2 mg/kg weekly for a total of 52 weeks. Trastuzumab treatment was permanently discontinued in patients who developed congestive heart failure, or persistent/recurrent LVEF decline [see Dosage and Administration (2.5)]. Radiation therapy, if administered, was initiated after the completion of chemotherapy. Patients with ER+ and/or PR+ tumors received hormonal therapy. The major efficacy outcome measure of the combined efficacy analysis was Disease-Free Survival (DFS), defined as the time from randomization to recurrence, occurrence of contralateral breast cancer, other second primary cancer, or death. An additional efficacy outcome measure was overall survival (OS).

A total of 3752 patients were included in the joint efficacy analysis of DFS following a median follow-up of 2.0 years in the AC → paclitaxel + trastuzumab arm. The pre-planned final OS analysis from the joint analysis included 4063 patients and was performed when 707 deaths had occurred after a median follow-up of 8.3 years in the AC → paclitaxel + trastuzumab arm. The data from both arms in NSABPB31 and two of the three study arms in NCCTG N9831 were pooled for efficacy analyses. The patients included in the DFS analysis had a median age of 49 years (range, 22 to 80 years; 6% > 65 years), 84% were White, 7% Black, 4% Hispanic, and 4% Asian/Pacific Islander. Disease characteristics included 90% infiltrating ductal histology, 38% T1, 91% nodal involvement, 27% intermediate and 66% high grade pathology, and 53% ER+ and/or PR+ tumors.

HERA:

In HERA, breast tumor specimens were required to show HER2 overexpression (3+ by IHC) or gene amplification (by FISH) as determined at a central laboratory. Patients with node-negative disease were required to have ≥ T1c primary tumor. Patients with a history of congestive heart failure or LVEF < 55%, uncontrolled arrhythmias, angina requiring medication, clinically significant valvular heart disease, evidence of transmural infarction on ECG, poorly controlled hypertension (systolic > 180 mm Hg or diastolic > 100 mm Hg) were not eligible.

Patients were randomized (1:1:1) upon completion of definitive surgery, and at least four cycles of chemotherapy to receive no additional treatment, or one year of trastuzumab treatment or two years of trastuzumab treatment. Patients undergoing a lumpectomy had also completed standard radiotherapy. Patients with ER+ and/or PgR+ disease received systemic adjuvant hormonal therapy at investigator discretion. Trastuzumab was administered with an initial dose of 8 mg/kg followed by subsequent doses of 6 mg/kg once every three weeks. The major efficacy outcome measure was Disease-Free Survival (DFS), defined as in NSABP B31 and NCCTG N9831. HERA was designed to compare one and two years of once every three week trastuzumab treatment versus observation in patients with HER2 positive EBC following surgery, established chemotherapy and radiotherapy (if applicable).

A protocol specified interim efficacy analysis comparing one-year trastuzumab treatment to observation was performed at a median follow-up duration of 12.6 months in the trastuzumab arm. Among the 3386 patients randomized to the observation (n = 1693) and trastuzumab one-year (n = 1693) treatment arms, the median age was 49 years (range 21 to 80), 83% were White, and 13% were Asian. Disease characteristics: 94% infiltrating ductal carcinoma, 50% ER+ and/or PgR+, 57% node positive, 32% node negative, and in 11% of patients, nodal status was not assessable due to prior neo-adjuvant chemotherapy. Ninety-six percent (1055/1098) of patients with node-negative disease had high-risk features: among the 1098 patients with node-negative disease, 49% (543) were ER− and PgR−, and 47% (512) were ER and/or PgR+ and had at least one of the following high-risk features: pathological tumor size greater than 2 cm, Grade 2 to 3, or age < 35 years. Prior to randomization, 94% of patients had received anthracycline-based chemotherapy regimens.

After the DFS results comparing observation to one-year trastuzumab treatment were disclosed, a prospectively planned analysis that included comparison of one year versus two years of trastuzumab treatment at a median follow-up duration of 8 years was performed. Based on this analysis, extending trastuzumab treatment for a duration of two years did not show additional benefit over treatment for one year [Hazard Ratios of two-years trastuzumab versus one-year trastuzumab treatment in the intent to treat (ITT) population for Disease-Free Survival (DFS) = 0.99 (95% CI: 0.87, 1.13), p-value = 0.90 and Overall Survival (OS) = 0.98 (0.83, 1.15); p-value = 0.78].

BCIRG006:

In BCIRG006, breast tumor specimens were required to show HER2 gene amplification (FISH+ only) as determined at a central laboratory. Patients were required to have either node-positive disease, or node-negative disease with at least one of the following high-risk features: ER/PR-negative, tumor size > 2 cm, age < 35 years, or histologic and/or nuclear Grade 2 or 3. Patients with a history of CHF, myocardial infarction, Grade 3 or 4 cardiac arrhythmia, angina requiring medication, clinically significant valvular heart disease, poorly controlled hypertension (diastolic > 100 mm Hg), any T4 or N2, or known N3 or M1 breast cancer were not eligible.

Patients were randomized (1:1:1) to receive doxorubicin and cyclophosphamide followed by docetaxel (AC-T), doxorubicin and cyclophosphamide followed by docetaxel plus trastuzumab (AC-TH), or docetaxel and carboplatin plus trastuzumab (TCH). In both the AC-T and AC-TH arms, doxorubicin 60 mg/m^2 and cyclophosphamide 600 mg/m^2 were administered every 3 weeks for four cycles; docetaxel 100 mg/m^2 was administered every 3 weeks for four cycles. In the TCH arm, docetaxel 75 mg/m^2 and carboplatin (at a target AUC of 6 mg/mL/min as a 30-to 60-minute infusion) were administered every 3 weeks for six cycles. Trastuzumab was administered weekly (initial dose of 4 mg/kg followed by weekly dose of 2 mg/kg) concurrently with either T or TC, and then every 3 weeks (6 mg/kg) as monotherapy for a total of 52 weeks. Radiation therapy, if administered, was initiated after completion of chemotherapy. Patients with ER+ and/or PR+ tumors received hormonal therapy. Disease-Free Survival (DFS) was the major efficacy outcome measure.

Among 3222 patients, the median age was 49 (range 22 to 74 years; 6% ≥ 65 years). Disease characteristics included 54% ER+ and/or PR+ and 71% node positive. Prior to randomization, all patients underwent primary surgery for breast cancer.

The results for DFS for the integrated analysis of NSABP B31 and NCCTG N9831, HERA, and BCIRG006 and OS results for the integrated analysis of NSABP B31 and NCCTG N9831, and HERA are presented in Table 9. For NSABP B31 and NCCTG N9831, the duration of DFS following a median follow-up of 2.0 years in the AC → TH arm is presented in Figure 4, and the duration of OS after a median follow-up of 8.3 years in the AC → TH arm is presented in Figure 5. The duration of DFS for BCIRG006 is presented in Figure 6. For NSABP B31 and NCCTG N9831, the OS hazard ratio was 0.64 (95% CI: 0.55, 0.74). At 8.3 years of median follow-up [AC → TH], the survival rate was estimated to be 86.9% in the AC → TH arm and 79.4% in the AC → T arm. The final OS analysis results from NSABP B31 and NCCTG N9831 indicate that OS benefit by age, hormone receptor status, number of positive lymph nodes, tumor size and grade, and surgery/radiation therapy was consistent with the treatment effect in the overall population. In patients ≤ 50 years of age (n = 2197), the OS hazard ratio was 0.65 (95% CI: 0.52, 0.81) and in patients > 50 years of age (n = 1866), the OS hazard ratio was 0.63 (95% CI: 0.51, 0.78). In the subgroup of patients with hormone receptor-positive disease (ER-positive and/or PR-positive) (n = 2223), the hazard ratio for OS was 0.63 (95% CI: 0.51, 0.78). In the subgroup of patients with hormone receptor-negative disease (ER-negative and PR-negative) (n = 1830), the hazard ratio for OS was 0.64 (95% CI: 0.52, 0.80). In the subgroup of patients with tumor size ≤ 2 cm (n = 1604), the hazard ratio for OS was 0.52 (95% CI: 0.39, 0.71). In the subgroup of patients with tumor size > 2 cm (n = 2448), the hazard ratio for OS was 0.67 (95% CI: 0.56, 0.80).

Table 9 Efficacy Results from Adjuvant Treatment of Breast Cancer (NSABP B31 and NCCTG N9831, HERA, and BCIRG006)
 | DFS events | DFS Hazard ratio (95% CI) p-value | Deaths (OS events) | OS Hazard ratio p-value
NSABP B31 and NCCTG N9831 [NSABP B31 and NCCTG N9831 regimens: doxorubicin and cyclophosphamide followed by paclitaxel (AC → T) or paclitaxel plus trastuzumab(AC → TH).]
AC → TH (n = 1872) [Efficacy evaluable population, for the primary DFS analysis, following a median follow-up of 2.0 years in the AC → TH arm.] (n = 2031) [Efficacy evaluable population, for the final OS analysis, following 707 deaths (8.3 years of median follow-up in the AC → TH arm).] | 133 | 0.48, [Hazard ratio estimated by Cox regression stratified by clinical trial, intended paclitaxel schedule, number of positive nodes, and hormone receptor status.] (0.39, 0.59) p< 0.0001 [stratified log-rank test.] | 289 | 0.64, (0.55, 0.74) p< 0.0001
AC → T (n = 1880) (n = 2032) | 261 |  | 418
HERA [At definitive DFS analysis with median duration of follow-up of 12.6 months in the one-year trastuzumab treatment arm.]
Chemo → Trastuzumab (n = 1693) | 127 | 0.54 (0.44, 0.67) p< 0.0001 [log-rank test.] | 31 | 0.75 p = NS [NS = non-significant.]
Chemo → Observation (n = 1693) | 219 |  | 40
BCIRG006 [BCIRG006 regimens: doxorubicin and cyclophosphamide followed by docetaxel (AC → T) or docetaxel plus trastuzumab (AC → TH); docetaxel and carboplatin plus trastuzumab (TCH).]
TCH (n = 1075) | 134 | 0.67 (0.54 to 0.84) p=0.0006, [A two-sided alpha level of 0.025 for each comparison.] | 56
AC → TH (n = 1074) | 121 | 0.60 (0.48 to 0.76) p< 0.0001, | 49
AC → T (n = 1073) | 180 |  | 80
CI = confidence interval.

Figure 4

Duration of Disease-Free Survival in Patients with Adjuvant Treatment of Breast Cancer (NSABP B31 and NCCTG N9831)

Figure 5

Overall Survival in Patients with Adjuvant Treatment of Breast Cancer (NSABP B31 and NCCTG N9831)

Figure 6

Disease-Free Survival in Patients with Adjuvant Treatment of Breast Cancer (BCIRG006)

Exploratory analyses of DFS as a function of HER2 overexpression or gene amplification were conducted for patients in NCCTG N9831 and HERA, where central laboratory testing data were available. The results are shown in Table 10. The number of events in NCCTG N9831 was small with the exception of the IHC 3+/FISH+ subgroup, which constituted 81% of those with data. Definitive conclusions cannot be drawn regarding efficacy within other subgroups due to the small number of events. The number of events in HERA was adequate to demonstrate significant effects on DFS in the IHC 3+/FISH unknown and the FISH +/IHC unknown subgroups.

Table 10 DFS in NCCTG N9831 and HERA for Patients with HER2 Overexpression or Amplification
 | NCCTG N9831 |  | HERA [Median follow-up duration of 12.6 months in the one-year trastuzumab treatment arm.]
HER2 Assay Result [IHC by HercepTest, FISH by PathVysion (HER2/CEP17 ratio ≥ 2.0) as performed at a central laboratory.] | Number of Patients | Hazard Ratio DFS (95% CI) | Number of Patients | Hazard Ratio DFS (95% CI)
IHC 3+
FISH (+) | 1170 | 0.42 (0.27, 0.64) | 91 | 0.56 (0.13, 2.50)
FISH (–) | 51 | 0.71 (0.04, 11.79) | 8 | —
FISH Unknown | 51 | 0.69 (0.09, 5.14) | 2258 | 0.53 (0.41, 0.69)
IHC < 3+ / FISH (+) | 174 | 1.01 (0.18, 5.65) | 299 [All cases in this category in HERA were IHC 2+.] | 0.53 (0.20, 1.42)
IHC unknown / FISH (+) | — | — | 724 | 0.59 (0.38, 0.93)

14.2 Metastatic Breast Cancer

The safety and efficacy of trastuzumab in treatment of women with metastatic breast cancer were studied in a randomized, controlled clinical trial in combination with chemotherapy (H0648g, n = 469 patients) and an open-label single agent clinical trial (H0649g, n = 222 patients). Both trials studied patients with metastatic breast cancer whose tumors overexpress the HER2 protein. Patients were eligible if they had 2 or 3 levels of overexpression (based on a 0 to 3 scale) by immunohistochemical assessment of tumor tissue performed by a central testing lab.

Previously Untreated Metastatic Breast Cancer (H0648g):

H0648g was a multicenter, randomized, open-label clinical trial conducted in 469 women with metastatic breast cancer who had not been previously treated with chemotherapy for metastatic disease. Tumor specimens were tested by IHC (Clinical Trial Assay, CTA) and scored as 0, 1+, 2+, or 3+, with 3+ indicating the strongest positivity. Only patients with 2+ or 3+ positive tumors were eligible (about 33% of those screened). Patients were randomized to receive chemotherapy alone or in combination with trastuzumab given intravenously as a 4 mg/kg loading dose followed by weekly doses of trastuzumab at 2 mg/kg. For those who had received prior anthracycline therapy in the adjuvant setting, chemotherapy consisted of paclitaxel (175 mg/m^2 over 3 hours every 21 days for at least six cycles); for all other patients, chemotherapy consisted of anthracycline plus cyclophosphamide (AC: doxorubicin 60 mg/m^2 or epirubicin 75 mg/m^2 plus 600 mg/m^2 cyclophosphamide every 21 days for six cycles). Sixty-five percent of patients randomized to receive chemotherapy alone in this study received trastuzumab at the time of disease progression as part of a separate extension study.

Based upon the determination by an independent Response Evaluation Committee, the patients randomized to trastuzumab and chemotherapy experienced a significantly longer median time to disease progression (TTP), a higher overall response rate (ORR), and a longer median duration of response (DoR) as compared with patients randomized to chemotherapy alone. Patients randomized to trastuzumab and chemotherapy also had a longer median overall survival (OS) (see Table 11). These treatment effects were observed both in patients who received trastuzumab plus paclitaxel and in those who received trastuzumab plus AC; however the magnitude of the effects was greater in the paclitaxel subgroup.

Table 11 H0648g: Efficacy Results in First-Line Treatment for Metastatic Breast Cancer
 | Combined Results |  | Paclitaxel Subgroup |  | AC Subgroup
 | Trastuzumab + All Chemo-therapy (n = 235) | All Chemo-therapy (n = 234) | Trastuzumab + Paclitaxel (n = 92) | Paclitaxel (n = 96) | Trastuzumab + AC [AC = Anthracycline (doxorubicin or epirubicin) and cyclophosphamide.] (n = 143) | AC (n = 138)
Time to Disease Progression (TTP)
Median (months) [Assessed by an independent Response Evaluation Committee.] , [Kaplan-Meier Estimate.] | 7.2 | 4.5 | 6.7 | 2.5 | 7.6 | 5.7
95% CI | 7, 8 | 4, 5 | 5, 10 | 2, 4 | 7, 9 | 5, 7
p-value [log-rank test.] | < 0.0001 |  | < 0.0001 |  | 0.002
Overall Response Rate (ORR)
Events (n) | 45 | 29 | 38 | 15 | 50 | 38
95% CI | 39, 51 | 23, 35 | 28, 48 | 8, 22 | 42, 58 | 30, 46
p-value [χ2-test.] | < 0.0001 |  | < 0.0001 |  | 0.10
Duration of Response (DoR)
Median (months), | 8.3 | 5.8 | 8.3 | 4.3 | 8.4 | 6.4
25%, 75% Quartile | 6, 15 | 4, 8 | 5, 11 | 4, 7 | 6, 15 | 4, 8
Overall Survival (OS)
Median (months) | 25.1 | 20.3 | 22.1 | 18.4 | 26.8 | 21.4
95% CI | 22, 30 | 17, 24 | 17, 29 | 13, 24 | 23, 33 | 18, 27
p-value | 0.05 |  | 0.17 |  | 0.16

Data from H0648g suggest that the beneficial treatment effects were largely limited to patients with the highest level of HER2 protein overexpression (3+) (see Table 12).

Table 12 Treatment Effects in H0648g as a Function of HER2 Overexpression or Amplification
HER2 Assay Result | Number of Patients (N) | Relative Risk [The relative risk represents the risk of progression or death in the trastuzumab plus chemotherapy arm versus the chemotherapy arm.] for Time to Disease Progression (95% CI) | Relative Risk for Mortality (95% CI)
CTA 2+ or 3+ | 469 | 0.49 (0.40, 0.61) | 0.80 (0.64, 1.00)
FISH (+) [FISH testing results were available for 451 of the 469 patients enrolled on study.] | 325 | 0.44 (0.34, 0.57) | 0.70 (0.53, 0.91)
FISH (−) | 126 | 0.62 (0.42, 0.94) | 1.06 (0.70, 1.63)
CTA 2+ | 120 | 0.76 (0.50, 1.15) | 1.26 (0.82, 1.94)
FISH (+) | 32 | 0.54 (0.21, 1.35) | 1.31 (0.53, 3.27)
FISH (−) | 83 | 0.77 (0.48, 1.25) | 1.11 (0.68, 1.82)
CTA 3+ | 349 | 0.42 (0.33, 0.54) | 0.70 (0.51, 0.90)
FISH (+) | 293 | 0.42 (0.32, 0.55) | 0.67 (0.51, 0.89)
FISH (−) | 43 | 0.43 (0.20, 0.94) | 0.88 (0.39, 1.98)

Previously Treated Metastatic Breast Cancer (H0649g):

Trastuzumab was studied as a single agent in a multicenter, open-label, single-arm clinical trial (H0649g) in patients with HER2 overexpressing metastatic breast cancer who had relapsed following one or two prior chemotherapy regimens for metastatic disease. Of 222 patients enrolled, 66% had received prior adjuvant chemotherapy, 68% had received two prior chemotherapy regimens for metastatic disease, and 25% had received prior myeloablative treatment with hematopoietic rescue. Patients were treated with a loading dose of 4 mg/kg IV followed by weekly doses of trastuzumab at 2 mg/kg IV.

The ORR (complete response + partial response), as determined by an independent Response Evaluation Committee, was 14%, with a 2% complete response rate and a 12% partial response rate. Complete responses were observed only in patients with disease limited to skin and lymph nodes. The overall response rate in patients whose tumors tested as CTA 3+ was 18% while in those that tested as CTA 2+, it was 6%.

14.3 Metastatic Gastric Cancer

The safety and efficacy of trastuzumab in combination with cisplatin and a fluoropyrimidine (capecitabine or 5-fluorouracil) were studied in patients previously untreated for metastatic gastric or gastroesophageal junction adenocarcinoma (ToGA). In this open-label, multi-center trial, 594 patients were randomized 1:1 to trastuzumab in combination with cisplatin and a fluoropyrimidine (FC+H) or chemotherapy alone (FC). Randomization was stratified by extent of disease (metastatic vs. locally advanced), primary site (gastric vs. gastroesophageal junction), tumor measurability (yes vs. no), ECOG performance status (0,1 vs. 2), and fluoropyrimidine (capecitabine vs. 5-fluorouracil). All patients were either HER2 gene amplified (FISH+) or HER2 overexpressing (IHC 3+). Patients were also required to have adequate cardiac function (e.g., LVEF > 50%).

On the trastuzumab-containing arm, trastuzumab was administered as an IV infusion at an initial dose of 8 mg/kg followed by 6 mg/kg every 3 weeks until disease progression. On both study arms cisplatin was administered at a dose of 80 mg/m^2 Day 1 every 3 weeks for 6 cycles as a 2 hour IV infusion. On both study arms, capecitabine was administered at 1000 mg/m^2 dose orally twice daily (total daily dose 2000 mg/m^2) for 14 days of each 21 day cycle for 6 cycles. Alternatively, continuous intravenous infusion (CIV) 5-fluorouracil was administered at a dose of 800 mg/m^2/day from Day 1 through Day 5 every three weeks for 6 cycles.

The median age of the study population was 60 years (range: 21−83); 76% were male; 53% were Asian, 38% Caucasian, 5% Hispanic, 5% other racial/ethnic groups; 91% had ECOG PS of 0 or 1; 82% had primary gastric cancer and 18% had primary gastroesophageal adenocarcinoma. Of these patients, 23% had undergone prior gastrectomy, 7% had received prior neoadjuvant and/or adjuvant therapy, and 2% had received prior radiotherapy.

The main outcome measure of ToGA was overall survival (OS), analyzed by the unstratified log-rank test. The final OS analysis based on 351 deaths was statistically significant (nominal significance level of 0.0193). An updated OS analysis was conducted at one year after the final analysis. The efficacy results of both the final and the updated analyses are summarized in Table 13 and Figure 7.

Table 13 Overall Survival in ToGA (ITT Population)
 | FC [FC = capecitabine vs. 5-fluorouracil] + Trastuzumab Arm N = 298 | FC Arm N = 296
Overall Survival (interim analysis)
N (%) | 167 (56.0%) | 184 (62.2%)
Median (months) | 13.5 | 11.0
95% CI | (11.7, 15.7) | (9.4, 12.5)
Hazard Ratio | 0.73
95% CI | (0.60, 0.91)
p-value [Two sided p-value comparing with the nominal significance level of 0.0193.] | 0.0038
Overall Survival (updated)
N (%) | 221 (74.2%) | 227 (76.7%)
Median (months) | 13.1 | 11.7
95% CI | (11.9, 15.1) | (10.3, 13.0)
Hazard Ratio | 0.80
95% CI | (0.67, 0.97)

Figure 7

Updated Overall Survival in Patients with Metastatic Gastric Cancer (ToGA)

An exploratory analysis of OS in patients based on HER2 gene amplification (FISH) and protein overexpression (IHC) testing is summarized in Table 14.

Table 14 Exploratory Analyses by HER2 Status Using Updated Overall Survival Results
 | FC (N = 296) [Two patients on the FC arm who were FISH+ but IHC status unknown were excluded from the exploratory subgroup analyses.] |  | FC+H (N = 298) [Five patients on the trastuzumab-containing arm who were FISH+, but IHC status unknown were excluded from the exploratory subgroup analyses.]
FISH+ / IHC 0, 1+ subgroup (N=133)
No. Deaths (%) / n (%) | 57/71 (80%) |  | 56/62 (90%)
Median OS Duration (mos.) | 8.8 |  | 8.3
95% CI (mos.) | (6.4, 11.7) |  | (6.2, 10.7)
Hazard ratio (95% CI) |  | 1.33 (0.92, 1.92)
FISH+ / IHC2+ subgroup (N=160)
No. Deaths (%) / n (%) | 65/80 (81%) |  | 64/80 (80%)
Median OS Duration (mos.) | 10.8 |  | 12.3
95% CI (mos.) | (6.8, 12.8) |  | (9.5, 15.7)
Hazard ratio (95% CI) |  | 0.78 (0.55, 1.10)
FISH+ or FISH- / IHC3+ [Includes 6 patients on chemotherapy arm, 10 patients on trastuzumab arm with FISH–, IHC3+ and 8 patients on chemotherapy arm, 8 patients on trastuzumab arm with FISH status unknown, IHC 3+.] subgroup (N=294)
No. Deaths (%) / n (%) | 104/143 (73%) |  | 96/151 (64%)
Median OS Duration (mos.) | 13.2 |  | 18.0
95% CI (mos.) | (11.5, 15.2) |  | (15.5, 21.2)
Hazard ratio (95% CI) |  | 0.66 (0.50, 0.87)

16 HOW SUPPLIED/STORAGE AND HANDLING

420 mg Multiple-dose vial

Ontruzant (trastuzumab-dttb) for injection 420 mg/vial is supplied in a multiple-dose vial as a white to pale yellow lyophilized sterile powder, under vacuum. Each carton contains one multiple-dose vial of Ontruzant and one vial (20 mL) of Bacteriostatic Water for Injection (BWFI), USP, containing 1.1% benzyl alcohol as a preservative.

NDC 78206-148-01.

150 mg Single-dose vial

Ontruzant (trastuzumab-dttb) for injection 150 mg/vial is supplied in a single-dose vial as a white to pale yellow lyophilized sterile powder, under vacuum. Each carton contains one single-dose vial of Ontruzant.

NDC 78206-147-01.

STORAGE AND HANDLING

Store Ontruzant vials in the refrigerator at 2° to 8°C (36° to 46°F) until time of reconstitution.

17 PATIENT COUNSELING INFORMATION

Cardiomyopathy

- Advise patients to contact a health care professional immediately for any of the following: new onset or worsening shortness of breath, cough, swelling of the ankles/legs, swelling of the face, palpitations, weight gain of more than 5 pounds in 24 hours, dizziness or loss of consciousness [see Boxed Warning: Cardiomyopathy].

Embryo-Fetal Toxicity

- Advise pregnant women and females of reproductive potential that Ontruzant exposure during pregnancy or within 7 months prior to conception can result in fetal harm. Advise female patients to contact their healthcare provider with a known or suspected pregnancy [see Use in Specific Populations (8.1)].
- Advise females of reproductive potential to use effective contraception during treatment and for 7 months following the last dose of Ontruzant [see Use in Specific Populations (8.3)].

Ontruzant [trastuzumab-dttb]

Manufactured by:
Samsung Bioepis Co., Ltd., 76, Songdogyoyuk-ro, Yeonsu-gu, Incheon, 21987, Republic of Korea
U.S. License No. 2046

Manufactured for:
Organon LLC, a subsidiary of Organon & Co., Jersey City, NJ 07302, USA
The trademarks above are owned by their respective owners.
Product of Denmark

Principal Display Panel - Ontruzant Carton Label

NDC 78206-147-01

150
mg/vial

Ontruzant®

(trastuzumab-dttb)
for injection

150 mg/vial

For Intravenous Infusion Only.

Must reconstitute and dilute
before intravenous infusion.

Single-dose vial.

Discard unused portion.

Rx only

ORGANON | SAMSUNG BIOEPIS

Principal Display Panel – Kit Label

NDC 78206-148-01

420
mg/vial

Ontruzant®

(trastuzumab-dttb)
for injection

420 mg/vial

For Intravenous Infusion Only.

Must reconstitute and dilute before
intravenous infusion.

Multiple-dose vial.

DO NOT FREEZE RECONSTITUTED SOLUTION.

KEEP REFRIGERATED.

Rx only

ORGANON | SAMSUNG BIOEPIS